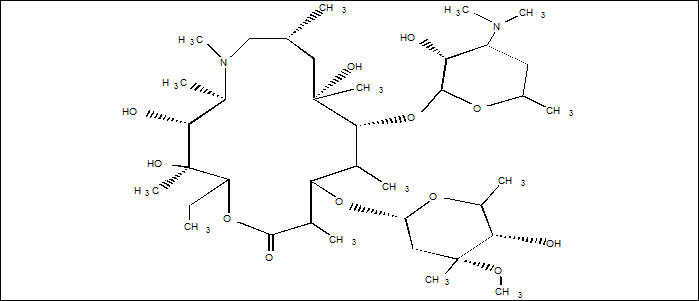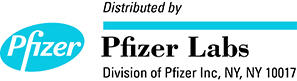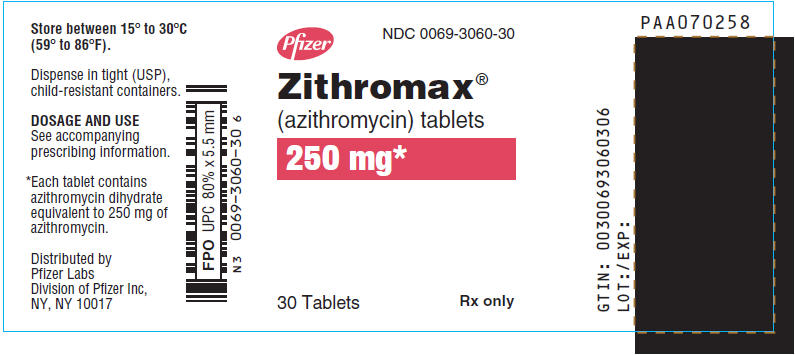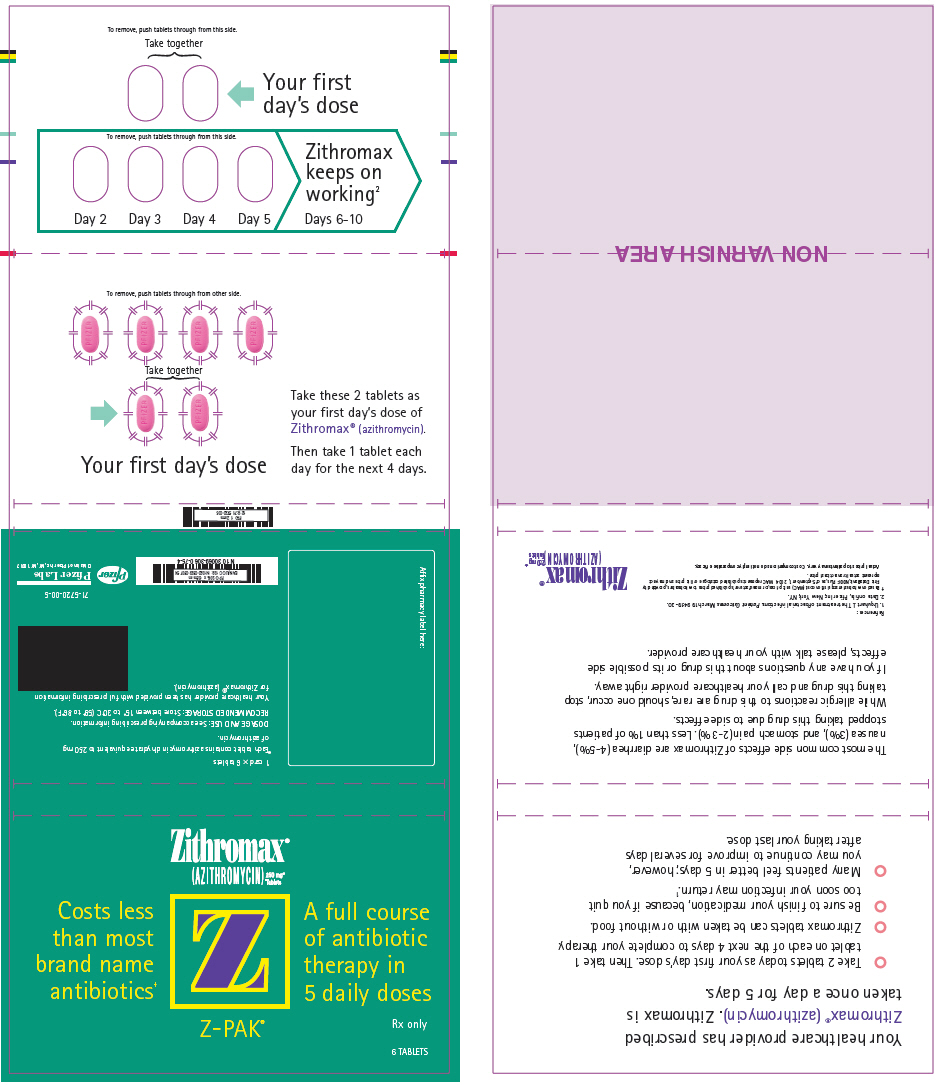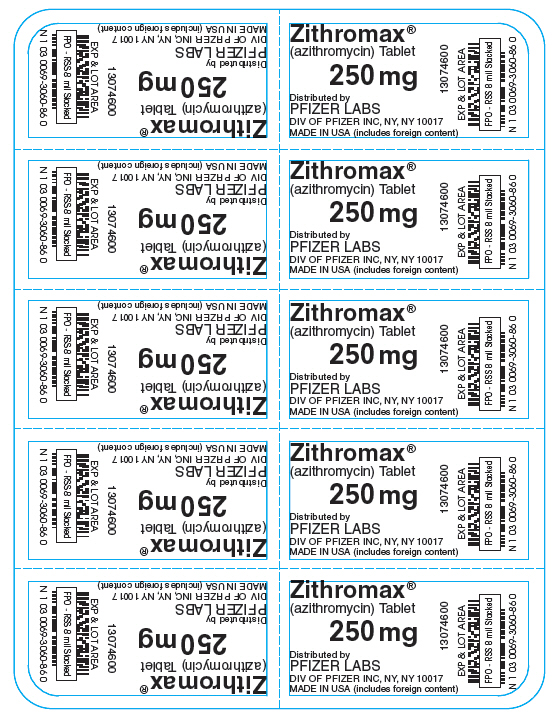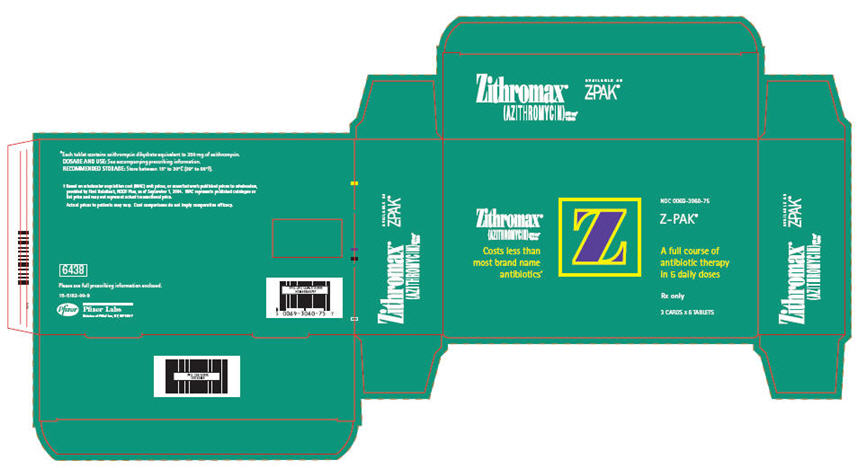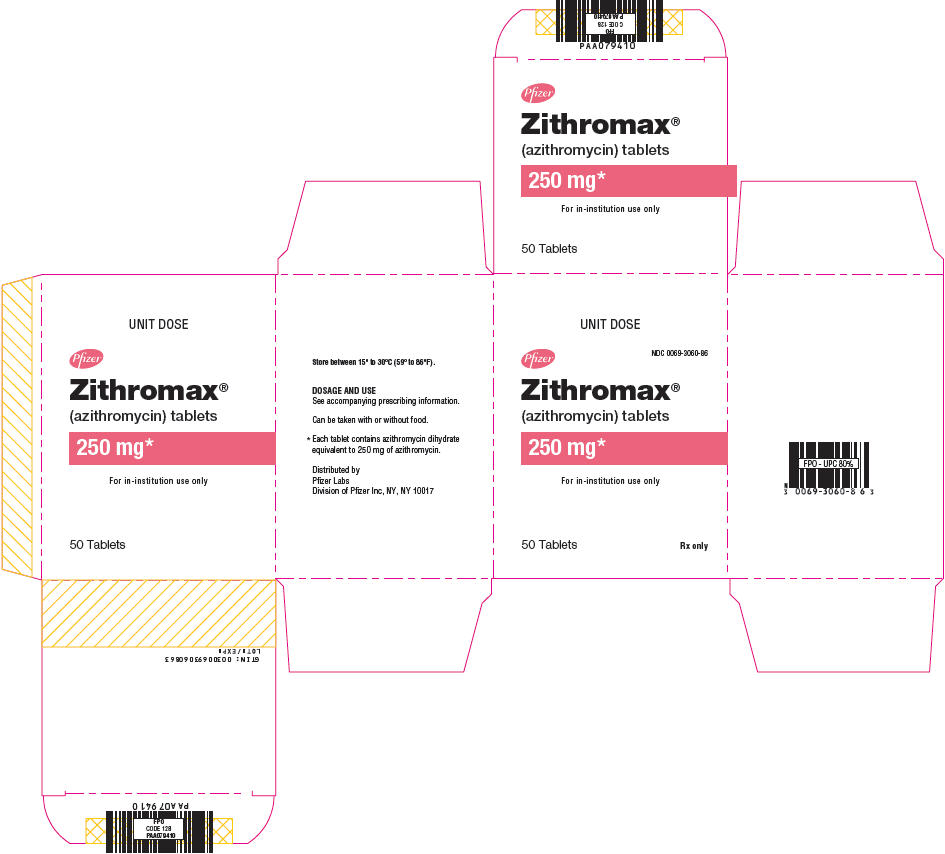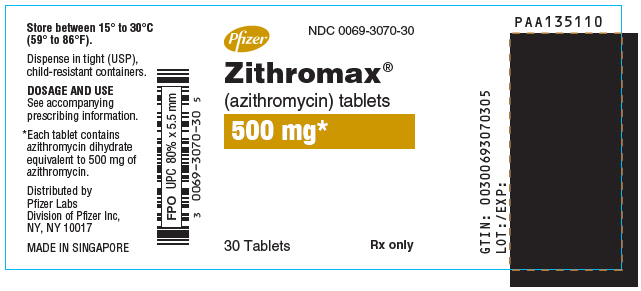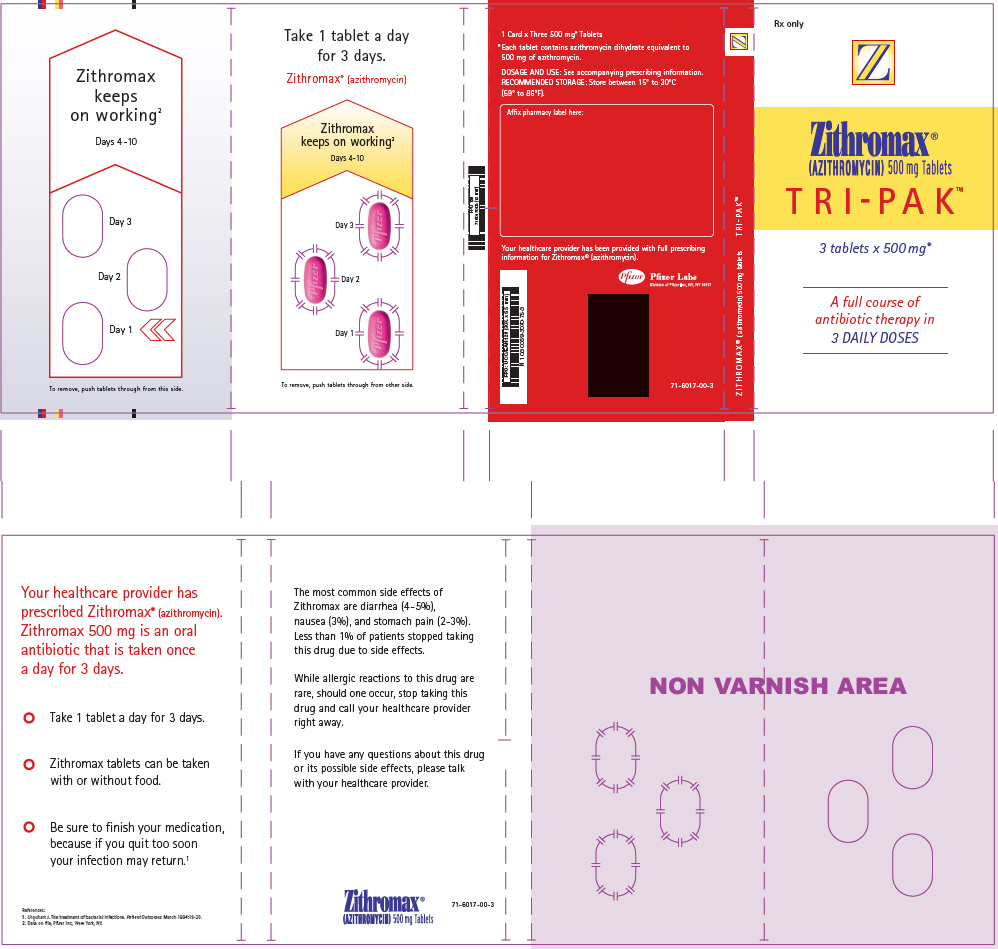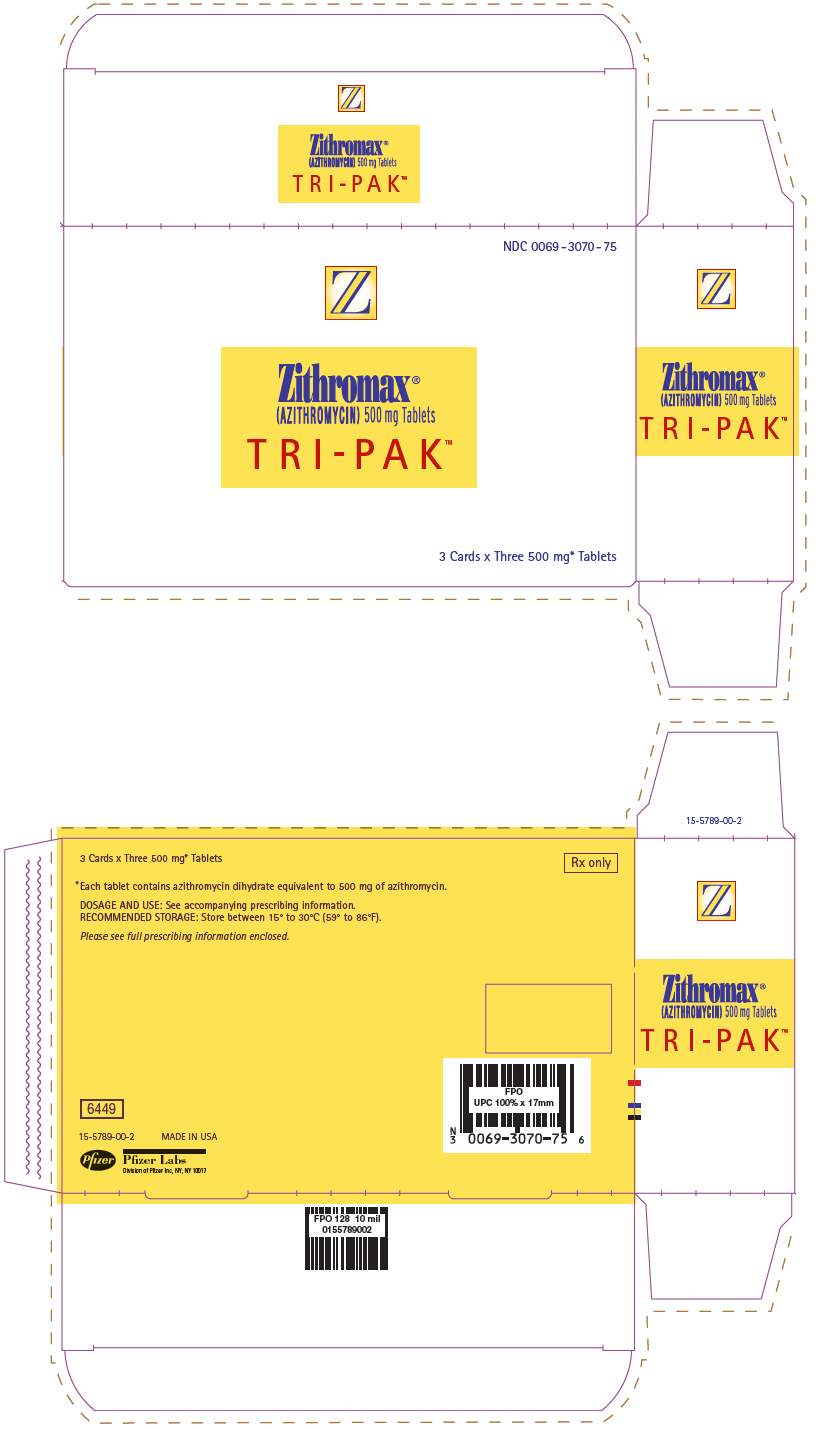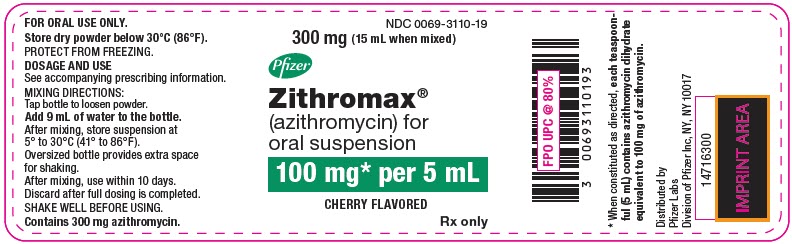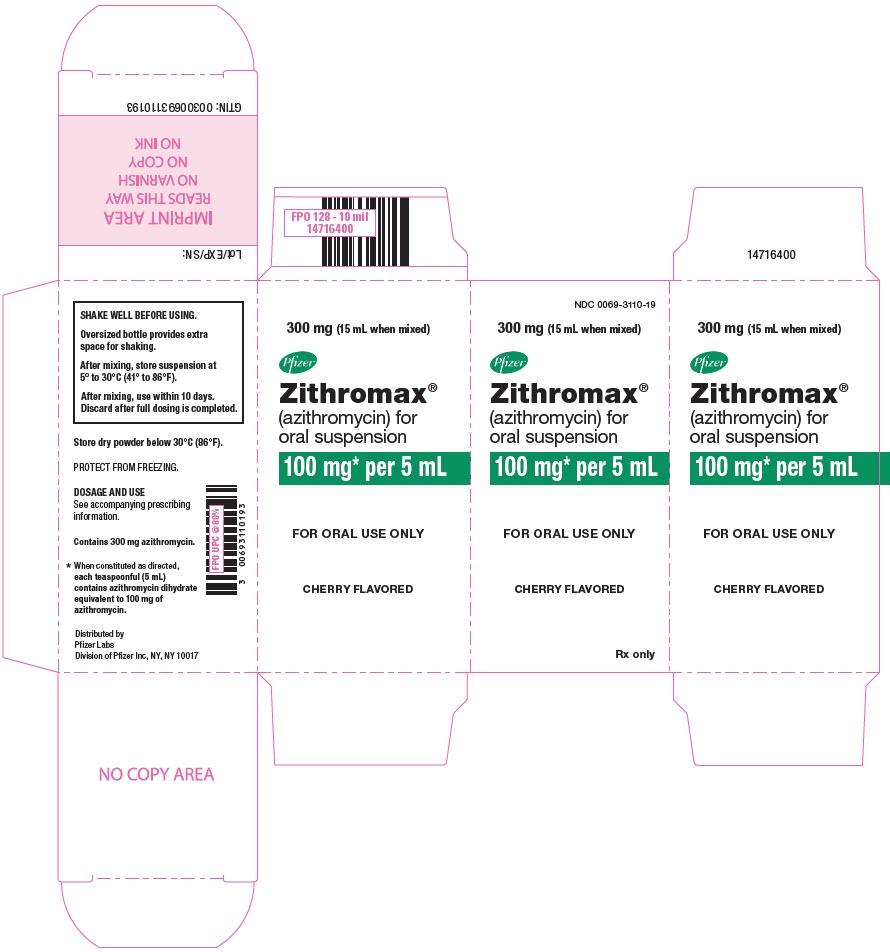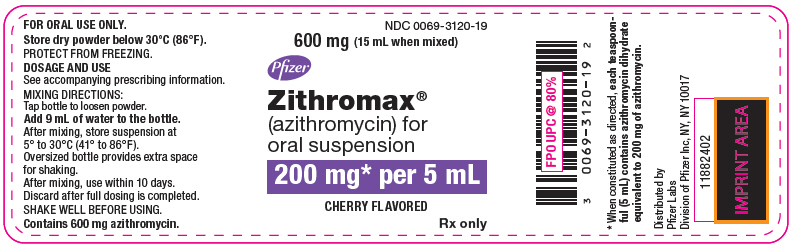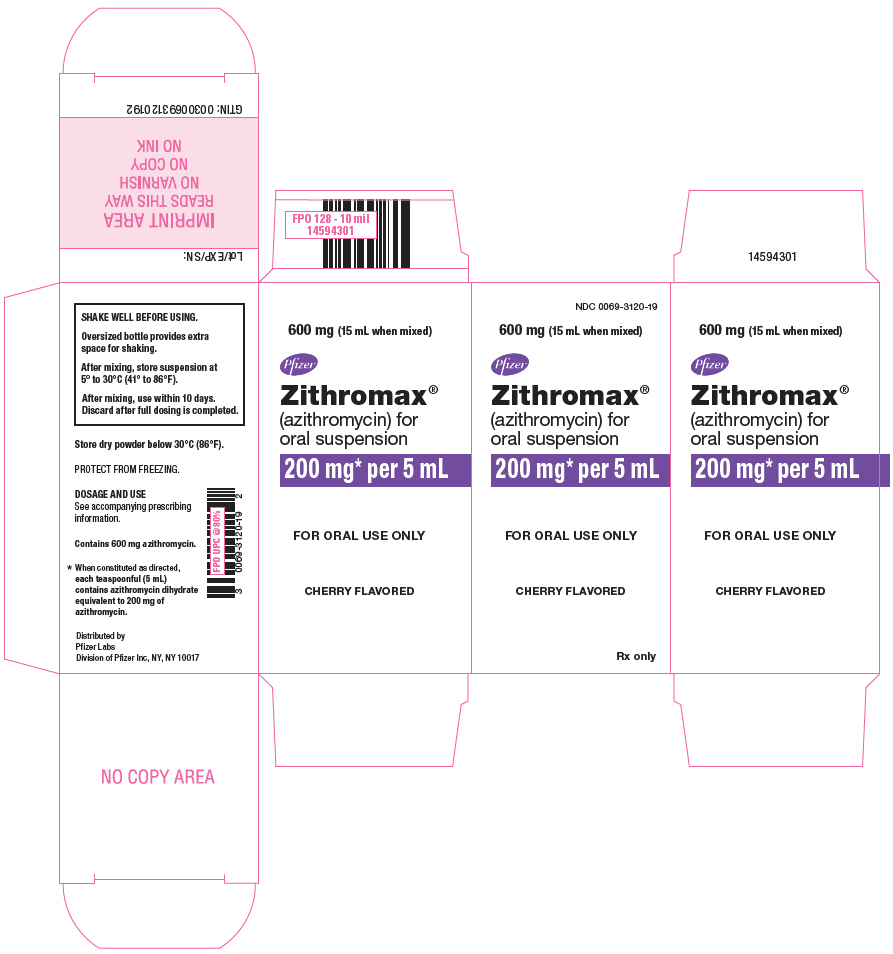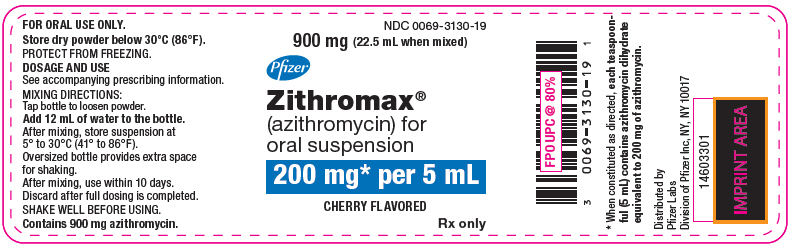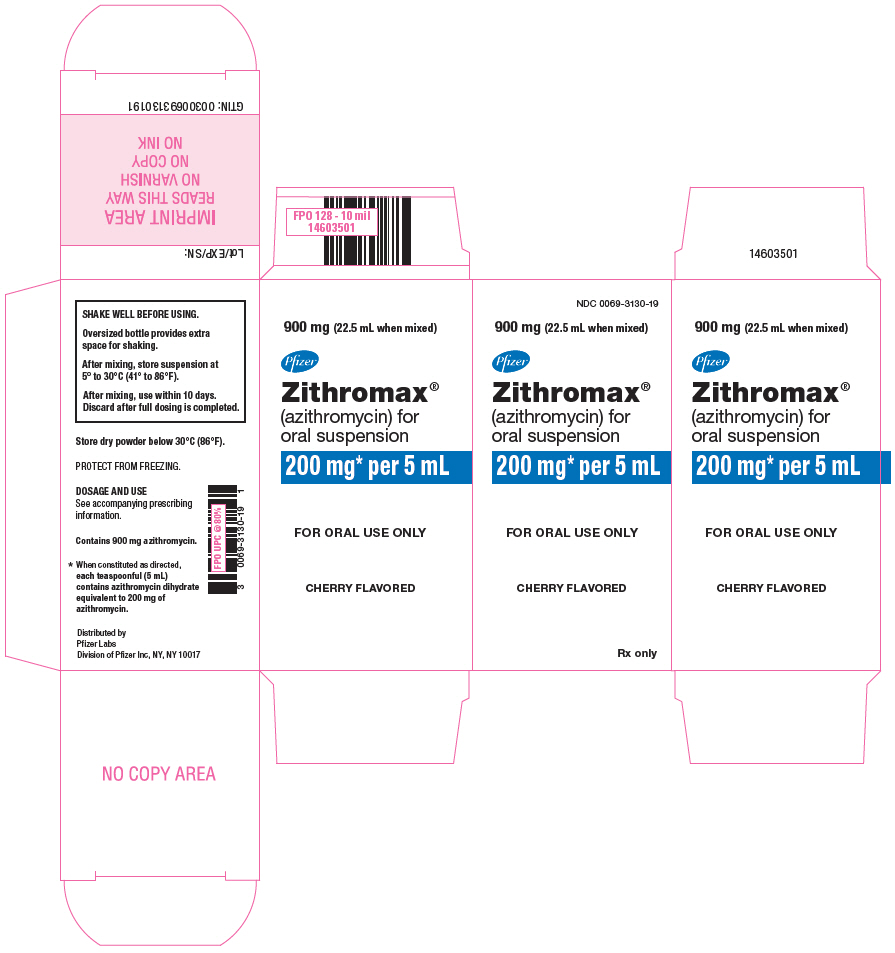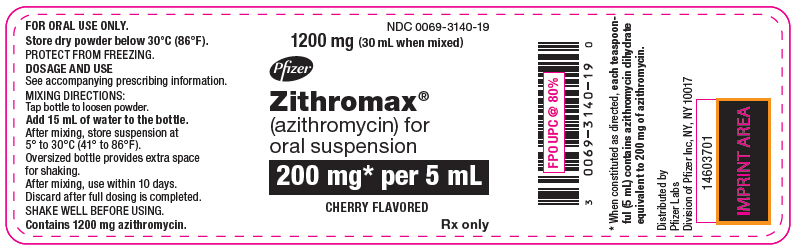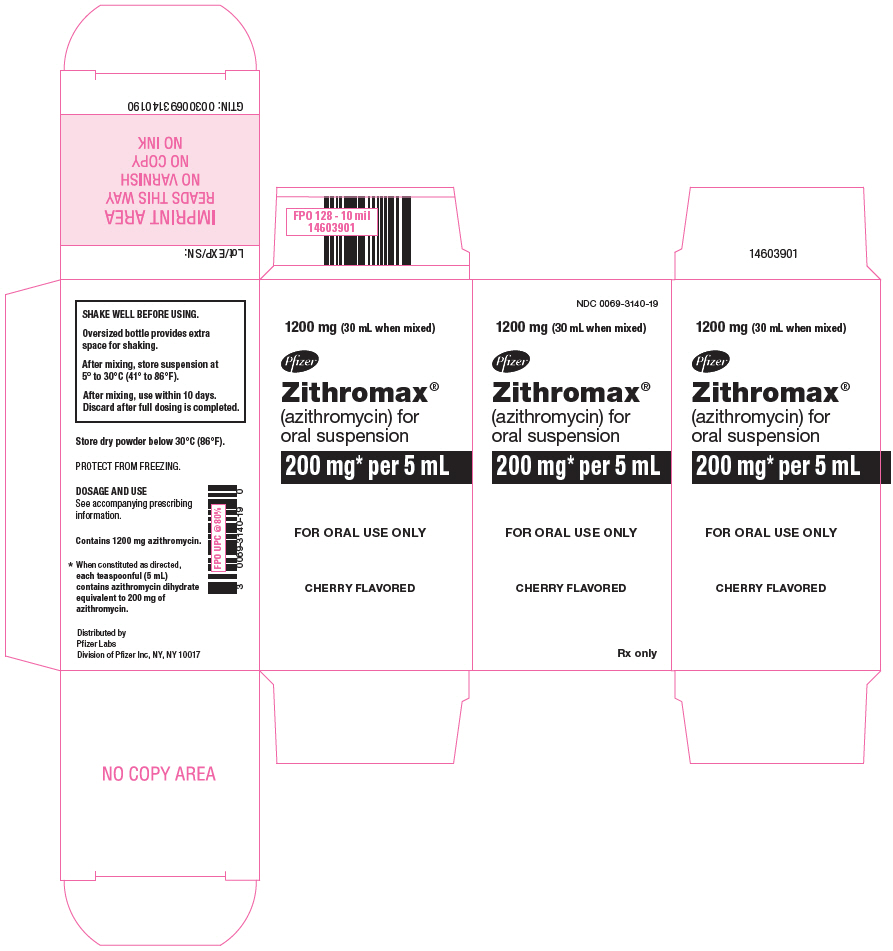 DRUG LABEL: Zithromax
NDC: 0069-3060 | Form: TABLET, FILM COATED
Manufacturer: Pfizer Laboratories Div Pfizer Inc
Category: prescription | Type: HUMAN PRESCRIPTION DRUG LABEL
Date: 20260107

ACTIVE INGREDIENTS: AZITHROMYCIN DIHYDRATE 250 mg/1 1
INACTIVE INGREDIENTS: ANHYDROUS DIBASIC CALCIUM PHOSPHATE; CROSCARMELLOSE SODIUM; MAGNESIUM STEARATE; SODIUM LAURYL SULFATE; HYPROMELLOSE, UNSPECIFIED; LACTOSE, UNSPECIFIED FORM; TITANIUM DIOXIDE; TRIACETIN; D&C RED NO. 30; ALUMINUM OXIDE

HIGHLIGHTS OF PRESCRIBING INFORMATION

These highlights do not include all the information needed to use ZITHROMAX® safely and effectively. See full prescribing information for ZITHROMAX.
ZITHROMAX (azithromycin) 250 mg and 500 mg tablets, for oral use
ZITHROMAX (azithromycin) for oral suspension
Initial U.S. Approval: 1991

RECENT MAJOR CHANGES

Warnings and Precautions, Cardiovascular Death (5.5) | 11/2021

1 INDICATIONS AND USAGE

ZITHROMAX is a macrolide antibacterial drug indicated for mild to moderate infections caused by designated, susceptible bacteria:

- Acute bacterial exacerbations of chronic bronchitis in adults (1.1)
- Acute bacterial sinusitis in adults (1.1)
- Uncomplicated skin and skin structure infections in adults (1.1)
- Urethritis and cervicitis in adults (1.1)
- Genital ulcer disease in men (1.1)
- Acute otitis media in pediatric patients (6 months of age and older) (1.2)
- Community-acquired pneumonia in adults and pediatric patients (6 months of age and older) (1.1, 1.2)
- Pharyngitis/tonsillitis in adults and pediatric patients (2 years of age and older) (1.1, 1.2)

Limitation of Use:

Azithromycin should not be used in patients with pneumonia who are judged to be inappropriate for oral therapy because of moderate to severe illness or risk factors. (1.3)

To reduce the development of drug-resistant bacteria and maintain the effectiveness of ZITHROMAX (azithromycin) and other antibacterial drugs, ZITHROMAX (azithromycin) should be used only to treat infections that are proven or strongly suspected to be caused by susceptible bacteria. (1.4)

2 DOSAGE AND ADMINISTRATION

- Adult Patients (2.1)

Infection | Recommended Dose/Duration of Therapy
Community-acquired pneumonia (mild severity) Pharyngitis/tonsillitis (second-line therapy) Skin/skin structure (uncomplicated) | 500 mg as a single dose on Day 1, followed by 250 mg once daily on Days 2 through 5.
Acute bacterial exacerbations of chronic bronchitis (mild to moderate) | 500 mg as a single dose on Day 1, followed by 250 mg once daily on Days 2 through 5 or 500 mg once daily for 3 days.
Acute bacterial sinusitis | 500 mg once daily for 3 days.
Genital ulcer disease (chancroid) Non-gonococcal urethritis and cervicitis | One single 1 gram dose.
Gonococcal urethritis and cervicitis | One single 2 gram dose.

- Pediatric Patients (2.2)

Infection | Recommended Dose/Duration of Therapy
Acute otitis media (6 months of age and older) | 30 mg/kg as a single dose or 10 mg/kg once daily for 3 days or 10 mg/kg as a single dose on Day 1 followed by 5 mg/kg/day on Days 2 through 5.
Acute bacterial sinusitis (6 months of age and older) | 10 mg/kg once daily for 3 days.
Community-acquired pneumonia (6 months of age and older) | 10 mg/kg as a single dose on Day 1 followed by 5 mg/kg once daily on Days 2 through 5.
Pharyngitis/tonsillitis (2 years of age and older) | 12 mg/kg once daily for 5 days.

3 DOSAGE FORMS AND STRENGTHS

- ZITHROMAX tablets 250 mg and 500 mg (3)
- ZITHROMAX for oral suspension 100 mg/5 mL and 200 mg/5 mL (3)

4 CONTRAINDICATIONS

- Patients with known hypersensitivity to azithromycin, erythromycin, any macrolide or ketolide drug. (4.1)
- Patients with a history of cholestatic jaundice/hepatic dysfunction associated with prior use of azithromycin. (4.2)

5 WARNINGS AND PRECAUTIONS

- Serious (including fatal) allergic and skin reactions: Discontinue ZITHROMAX if reaction occurs. (5.1)
- Hepatotoxicity: Severe, and sometimes fatal, hepatotoxicity has been reported. Discontinue ZITHROMAX immediately if signs and symptoms of hepatitis occur. (5.2)
- Infantile Hypertrophic Pyloric Stenosis (IHPS): Following the use of azithromycin in neonates (treatment up to 42 days of life), IHPS has been reported. Direct parents and caregivers to contact their physician if vomiting or irritability with feeding occurs. (5.3)
- Prolongation of QT interval and cases of torsades de pointes have been reported. This risk which can be fatal should be considered in patients with certain cardiovascular disorders including known QT prolongation or history torsades de pointes, those with proarrhythmic conditions, and with other drugs that prolong the QT interval. (5.4)
- Cardiovascular Death: Some observational studies have shown an approximately two-fold increased short-term potential risk of acute cardiovascular death in adults exposed to azithromycin relative to other antibacterial drugs, including amoxicillin. Consider balancing this potential risk with treatment benefits when prescribing ZITHROMAX. (5.5)
- Clostridioides difficile-Associated Diarrhea: Evaluate patients if diarrhea occurs. (5.6)
- ZITHROMAX may exacerbate muscle weakness in persons with myasthenia gravis. (5.7)

6 ADVERSE REACTIONS

Most common adverse reactions are diarrhea (5 to 14%), nausea (3 to 18%), abdominal pain (3 to 7%), or vomiting (2 to 7%). (6.1)

To report SUSPECTED ADVERSE REACTIONS, contact Pfizer Inc. at 1-800-438-1985 or FDA at 1-800-FDA-1088 or www.fda.gov/medwatch.

7 DRUG INTERACTIONS

- Nelfinavir: Close monitoring for known adverse reactions of azithromycin, such as liver enzyme abnormalities and hearing impairment, is warranted. (7.1)
- Warfarin: Use with azithromycin may increase coagulation times; monitor prothrombin time. (7.2)

8 USE IN SPECIFIC POPULATIONS

- Pediatric use: Safety and effectiveness in the treatment of patients under 6 months of age have not been established. (8.4)
- Geriatric use: Elderly patients may be more susceptible to development of torsades de pointes arrhythmias. (8.5)

FULL PRESCRIBING INFORMATION

1 INDICATIONS AND USAGE

ZITHROMAX (azithromycin) is a macrolide antibacterial drug indicated for the treatment of patients with mild to moderate infections caused by susceptible strains of the designated microorganisms in the specific conditions listed below. Recommended dosages and durations of therapy in adult and pediatric patient populations vary in these indications. [see Dosage and Administration (2)]

1.1 Adult Patients

- Acute bacterial exacerbations of chronic bronchitis due to Haemophilus influenzae, Moraxella catarrhalis, or Streptococcus pneumoniae.
- Acute bacterial sinusitis due to Haemophilus influenzae, Moraxella catarrhalis. or Streptococcus pneumoniae.
- Community-acquired pneumonia due to Chlamydophila pneumoniae, Haemophilus influenzae, Mycoplasma pneumoniae, or Streptococcus pneumoniae in patients appropriate for oral therapy.
- Pharyngitis/tonsillitis caused by Streptococcus pyogenes as an alternative to first-line therapy in individuals who cannot use first-line therapy.
- Uncomplicated skin and skin structure infections due to Staphylococcus aureus, Streptococcus pyogenes, or Streptococcus agalactiae.
- Urethritis and cervicitis due to Chlamydia trachomatis or Neisseria gonorrhoeae.
- Genital ulcer disease in men due to Haemophilus ducreyi (chancroid). Due to the small number of women included in clinical trials, the efficacy of azithromycin in the treatment of chancroid in women has not been established.

1.2 Pediatric Patients

[see Use in Specific Populations (8.4) and Clinical Studies (14.2)]

- Acute otitis media (>6 months of age) caused by Haemophilus influenzae, Moraxella catarrhalis, or Streptococcus pneumoniae.
- Community-acquired pneumonia (>6 months of age) due to Chlamydophila pneumoniae, Haemophilus influenzae, Mycoplasma pneumoniae, or Streptococcus pneumoniae in patients appropriate for oral therapy.
- Pharyngitis/tonsillitis (>2 years of age) caused by Streptococcus pyogenes as an alternative to first-line therapy in individuals who cannot use first-line therapy.

1.3 Limitations of Use

Azithromycin should not be used in patients with pneumonia who are judged to be inappropriate for oral therapy because of moderate to severe illness or risk factors such as any of the following:

- patients with cystic fibrosis,
- patients with nosocomial infections,
- patients with known or suspected bacteremia,
- patients requiring hospitalization,
- elderly or debilitated patients, or
- patients with significant underlying health problems that may compromise their ability to respond to their illness (including immunodeficiency or functional asplenia).

1.4 Usage

To reduce the development of drug-resistant bacteria and maintain the effectiveness of ZITHROMAX (azithromycin) and other antibacterial drugs, ZITHROMAX (azithromycin) should be used only to treat infections that are proven or strongly suspected to be caused by susceptible bacteria. When culture and susceptibility information are available, they should be considered in selecting or modifying antibacterial therapy. In the absence of such data, local epidemiology and susceptibility patterns may contribute to the empiric selection of therapy.

2 DOSAGE AND ADMINISTRATION

2.1 Adult Patients

[see Indications and Usage (1.1) and Clinical Pharmacology (12.3)]

Infection [DUE TO THE INDICATED ORGANISMS [see Indications and Usage (1.1)]] | Recommended Dose/Duration of Therapy
Community-acquired pneumonia Pharyngitis/tonsillitis (second-line therapy) Skin/skin structure (uncomplicated) | 500 mg as a single dose on Day 1, followed by 250 mg once daily on Days 2 through 5
Acute bacterial exacerbations of chronic obstructive pulmonary disease | 500 mg once daily for 3 days OR 500 mg as a single dose on Day 1, followed by 250 mg once daily on Days 2 through 5
Acute bacterial sinusitis | 500 mg once daily for 3 days
Genital ulcer disease (chancroid) | One single 1 gram dose
Non-gonococcal urethritis and cervicitis | One single 1 gram dose
Gonococcal urethritis and cervicitis | One single 2 gram dose

ZITHROMAX tablets can be taken with or without food.

2.2 Pediatric Patients^1

Infection [DUE TO THE INDICATED ORGANISMS [see Indications and Usage (1.2)]] | Recommended Dose/Duration of Therapy
Acute otitis media | 30 mg/kg as a single dose or 10 mg/kg once daily for 3 days or 10 mg/kg as a single dose on Day 1 followed by 5 mg/kg/day on Days 2 through 5.
Acute bacterial sinusitis | 10 mg/kg once daily for 3 days.
Community-acquired pneumonia | 10 mg/kg as a single dose on Day 1 followed by 5 mg/kg once daily on Days 2 through 5.
Pharyngitis/tonsillitis | 12 mg/kg once daily for 5 days.
^1 see dosing tables below for maximum doses evaluated by indication

ZITHROMAX for oral suspension can be taken with or without food.

PEDIATRIC DOSAGE GUIDELINES FOR OTITIS MEDIA, ACUTE BACTERIAL SINUSITIS, AND COMMUNITY-ACQUIRED PNEUMONIA
(Age 6 months and above, [see Use in Specific Populations (8.4)])
Based on Body Weight

OTITIS MEDIA AND COMMUNITY-ACQUIRED PNEUMONIA: (5-Day Regimen) [Effectiveness of the 3-day or 1-day regimen in pediatric patients with community-acquired pneumonia has not been established.]
Dosing Calculated on 10 mg/kg/day Day 1 and 5 mg/kg/day Days 2 to 5.
Weight | 100 mg/5 mL |  | 200 mg/5 mL |  | Total mL per Treatment Course | Total mg per Treatment Course
Kg | Day 1 | Days 2–5 | Day 1 | Days 2-5 | Total mL per Treatment Course | Total mg per Treatment Course
5 | 2.5 mL; (½ tsp) | 1.25 mL;(¼ tsp) |  |  | 7.5 mL | 150 mg
10 | 5 mL; (1tsp) | 2.5 mL; (½ tsp) |  |  | 15 mL | 300 mg
20 |  |  | 5 mL; (1 tsp) | 2.5 mL; (½ tsp) | 15 mL | 600 mg
30 |  |  | 7.5 mL; (1½ tsp) | 3.75 mL; (¾ tsp) | 22.5 mL | 900 mg
40 |  |  | 10 mL; (2 tsp) | 5 mL; (1 tsp) | 30 mL | 1200 mg
50 and above |  |  | 12.5 mL; (2½ tsp) | 6.25 mL; (1¼ tsp) | 37.5 mL | 1500 mg

OTITIS MEDIA AND ACUTE BACTERIAL SINUSITIS: (3-Day Regimen) [Effectiveness of the 5-day or 1-day regimen in pediatric patients with acute bacterial sinusitis has not been established.]
Dosing Calculated on 10 mg/kg/day.
Weight | 100 mg/5 mL | 200 mg/5 mL | Total mL per Treatment Course | Total mg per Treatment Course
Kg | Days 1–3 | Days 1–3 | Total mL per Treatment Course | Total mg per Treatment Course
5 | 2.5 mL; (1/2 tsp) |  | 7.5 mL | 150 mg
10 | 5 mL; (1 tsp) |  | 15 mL | 300 mg
20 |  | 5 mL (1 tsp) | 15 mL | 600 mg
30 |  | 7.5 mL (1½ tsp) | 22.5 mL | 900 mg
40 |  | 10 mL (2 tsp) | 30 mL | 1200 mg
50 and above |  | 12.5 mL (2 ½ tsp) | 37.5 mL | 1500 mg

OTITIS MEDIA: (1-Day Regimen)
Dosing Calculated on 30 mg/kg as a single dose.
Weight | 200 mg/5 mL | Total mL per Treatment Course | Total mg per Treatment Course
Kg | 1-Day Regimen | Total mL per Treatment Course | Total mg per Treatment Course
5 | 3.75 mL;(3/4 tsp) | 3.75 mL | 150 mg
10 | 7.5 mL;(1½ tsp) | 7.5 mL | 300 mg
20 | 15 mL;(3 tsp) | 15 mL | 600 mg
30 | 22.5 mL;(4½ tsp) | 22.5 mL | 900 mg
40 | 30 mL;(6 tsp) | 30 mL | 1200 mg
50 and above | 37.5 mL;(7½ tsp) | 37.5 mL | 1500 mg

The safety of re-dosing azithromycin in pediatric patients who vomit after receiving 30 mg/kg as a single dose has not been established. In clinical studies involving 487 patients with acute otitis media given a single 30 mg/kg dose of azithromycin, 8 patients who vomited within 30 minutes of dosing were re-dosed at the same total dose.

Pharyngitis/Tonsillitis: The recommended dose of ZITHROMAX for children with pharyngitis/tonsillitis is 12 mg/kg once daily for 5 days. (See chart below.)

PEDIATRIC DOSAGE GUIDELINES FOR PHARYNGITIS/TONSILLITIS
(Age 2 years and above, [see Use in Specific Populations (8.4)])
Based on Body Weight

PHARYNGITIS/TONSILLITIS: (5-Day Regimen)
Dosing Calculated on 12 mg/kg/day for 5 days.
Weight | 200 mg/5 mL | Total mL per Treatment Course | Total mg per Treatment Course
Kg | Day 1–5 | Total mL per Treatment Course | Total mg per Treatment Course
8 | 2.5 mL; (½ tsp) | 12.5 mL | 500 mg
17 | 5 mL; (1 tsp) | 25 mL | 1000 mg
25 | 7.5 mL; (1½ tsp) | 37.5 mL | 1500 mg
33 | 10 mL; (2 tsp) | 50 mL | 2000 mg
40 | 12.5 mL; (2½ tsp) | 62.5 mL | 2500 mg

Constituting instructions for ZITHROMAX Oral Suspension 300, 600, 900, 1200 mg bottles. The table below indicates the volume of water to be used for constitution:

Amount of water to be added | Total volume after constitution (azithromycin content) | Azithromycin concentration after constitution
9 mL (300 mg) | 15 mL (300 mg) | 100 mg/5 mL
9 mL (600 mg) | 15 mL (600 mg) | 200 mg/5 mL
12 mL (900 mg) | 22.5 mL (900 mg) | 200 mg/5 mL
15 mL (1200 mg) | 30 mL (1200 mg) | 200 mg/5 mL

Shake well before each use. Oversized bottle provides shake space. Keep tightly closed.

After mixing, store suspension at 5° to 30°C (41° to 86°F) and use within 10 days. Discard after full dosing is completed.

3 DOSAGE FORMS AND STRENGTHS

ZITHROMAX 250 mg tablets are supplied as pink modified capsular shaped, engraved, film-coated tablets containing azithromycin dihydrate equivalent to 250 mg of azithromycin. ZITHROMAX 250 mg tablets are engraved with "PFIZER" on one side and "306" on the other, or "Pfizer" on one side and "ZTM 250" on the other. These are packaged in bottles and blister cards of 6 tablets (Z-PAKS®).

ZITHROMAX 500 mg tablets are supplied as pink modified capsular shaped, engraved, film-coated tablets containing azithromycin dihydrate equivalent to 500 mg of azithromycin. ZITHROMAX 500 mg tablets are engraved with "Pfizer" on one side and "ZTM500" on the other. These are packaged in bottles and blister cards of 3 tablets (TRI-PAKS™).

ZITHROMAX for oral suspension after constitution contains a flavored suspension. ZITHROMAX for oral suspension is supplied to provide 100 mg/5 mL or 200 mg/5 mL suspension in bottles.

4 CONTRAINDICATIONS

4.1 Hypersensitivity

ZITHROMAX is contraindicated in patients with known hypersensitivity to azithromycin, erythromycin, any macrolide or ketolide drug.

4.2 Hepatic Dysfunction

ZITHROMAX is contraindicated in patients with a history of cholestatic jaundice/hepatic dysfunction associated with prior use of azithromycin.

5 WARNINGS AND PRECAUTIONS

5.1 Hypersensitivity

Serious allergic reactions, including angioedema, anaphylaxis, and dermatologic reactions including Acute Generalized Exanthematous Pustulosis (AGEP), Stevens-Johnson syndrome, and toxic epidermal necrolysis have been reported in patients on azithromycin therapy. [see Contraindications (4.1)]

Fatalities have been reported. Cases of Drug Reaction with Eosinophilia and Systemic Symptoms (DRESS) have also been reported. Despite initially successful symptomatic treatment of the allergic symptoms, when symptomatic therapy was discontinued, the allergic symptoms recurred soon thereafter in some patients without further azithromycin exposure. These patients required prolonged periods of observation and symptomatic treatment. The relationship of these episodes to the long tissue half-life of azithromycin and subsequent prolonged exposure to antigen is presently unknown.

If an allergic reaction occurs, the drug should be discontinued and appropriate therapy should be instituted. Physicians should be aware that allergic symptoms may reappear when symptomatic therapy has been discontinued.

5.2 Hepatotoxicity

Abnormal liver function, hepatitis, cholestatic jaundice, hepatic necrosis, and hepatic failure have been reported, some of which have resulted in death. Discontinue azithromycin immediately if signs and symptoms of hepatitis occur.

5.3 Infantile Hypertrophic Pyloric Stenosis (IHPS)

Following the use of azithromycin in neonates (treatment up to 42 days of life), IHPS has been reported. Direct parents and caregivers to contact their physician if vomiting or irritability with feeding occurs.

5.4 QT Prolongation

Prolonged cardiac repolarization and QT interval, imparting a risk of developing cardiac arrhythmia and torsades de pointes, have been seen with treatment with macrolides, including azithromycin. Cases of torsades de pointes have been spontaneously reported during postmarketing surveillance in patients receiving azithromycin. Providers should consider the risk of QT prolongation which can be fatal when weighing the risks and benefits of azithromycin for at-risk groups including:

- patients with known prolongation of the QT interval, a history of torsades de pointes, congenital long QT syndrome, bradyarrhythmias or uncompensated heart failure
- patients on drugs known to prolong the QT interval
- patients with ongoing proarrhythmic conditions such as uncorrected hypokalemia or hypomagnesemia, clinically significant bradycardia, and in patients receiving Class IA (quinidine, procainamide) or Class III (dofetilide, amiodarone, sotalol) antiarrhythmic agents.

Elderly patients may be more susceptible to drug-associated effects on the QT interval.

5.5 Cardiovascular Death

Some observational studies have shown an approximately two-fold increased short-term potential risk of acute cardiovascular death in adults exposed to azithromycin relative to other antibacterial drugs, including amoxicillin. The five-day cardiovascular mortality observed in these studies ranged from 20 to 400 per million azithromycin treatment courses. This potential risk was noted to be greater during the first five days of azithromycin use and does not appear to be limited to those patients with preexisting cardiovascular diseases. The data in these observational studies are insufficient to establish or exclude a causal relationship between acute cardiovascular death and azithromycin use. Consider balancing this potential risk with treatment benefits when prescribing ZITHROMAX.

5.6 Clostridioides difficile-Associated Diarrhea (CDAD)

Clostridioides difficile-associated diarrhea has been reported with use of nearly all antibacterial agents, including ZITHROMAX, and may range in severity from mild diarrhea to fatal colitis. Treatment with antibacterial agents alters the normal flora of the colon, leading to overgrowth of C. difficile.

C. difficile produces toxins A and B which contribute to the development of CDAD. Hypertoxin producing strains of C. difficile cause increased morbidity and mortality, as these infections can be refractory to antibacterial therapy and may require colectomy. CDAD must be considered in all patients who present with diarrhea following antibiotic use. Careful medical history is necessary since CDAD has been reported to occur over two months after the administration of antibacterial agents.

If CDAD is suspected or confirmed, ongoing antibiotic use not directed against C. difficile may need to be discontinued. Appropriate fluid and electrolyte management, protein supplementation, antibiotic treatment of C. difficile, and surgical evaluation should be instituted as clinically indicated.

5.7 Exacerbation of Myasthenia Gravis

Exacerbation of symptoms of myasthenia gravis and new onset of myasthenic syndrome have been reported in patients receiving azithromycin therapy.

5.8 Use in Sexually Transmitted Infections

ZITHROMAX, at the recommended dose, should not be relied upon to treat syphilis. Antibacterial agents used to treat non-gonococcal urethritis may mask or delay the symptoms of incubating syphilis. All patients with sexually transmitted urethritis or cervicitis should have a serologic test for syphilis and appropriate testing for gonorrhea performed at the time of diagnosis. Appropriate antibacterial therapy and follow-up tests for these diseases should be initiated if infection is confirmed.

5.9 Development of Drug-Resistant Bacteria

Prescribing ZITHROMAX in the absence of a proven or strongly suspected bacterial infection is unlikely to provide benefit to the patient and increases the risk of the development of drug-resistant bacteria.

6 ADVERSE REACTIONS

The following clinically significant adverse reactions are described elsewhere in labeling:

- Hypersensitivity [see Warnings and Precautions (5.1)]
- Hepatotoxicity [see Warnings and Precautions (5.2)]
- Infantile Hypertrophic Pyloric Stenosis (IHPS) [see Warnings and Precautions (5.3)]
- QT Prolongation [see Warnings and Precautions (5.4)]
- Cardiovascular Death [see Warnings and Precautions (5.5)]
- Clostridioides difficile-Associated Diarrhea (CDAD) [see Warnings and Precautions (5.6)]
- Exacerbation of Myasthenia Gravis [see Warnings and Precautions (5.7)]

6.1 Clinical Trials Experience

Because clinical trials are conducted under widely varying conditions, adverse reaction rates observed in the clinical trials of a drug cannot be directly compared to rates in the clinical trials of another drug and may not reflect the rates observed in practice.

In clinical trials, most of the reported side effects were mild to moderate in severity and were reversible upon discontinuation of the drug. Potentially serious adverse reactions of angioedema and cholestatic jaundice were reported. Approximately 0.7% of the patients (adults and pediatric patients) from the 5-day multiple-dose clinical trials discontinued ZITHROMAX (azithromycin) therapy because of treatment-related adverse reactions. In adults given 500 mg/day for 3 days, the discontinuation rate due to treatment-related adverse reactions was 0.6%. In clinical trials in pediatric patients given 30 mg/kg, either as a single dose or over 3 days, discontinuation from the trials due to treatment-related adverse reactions was approximately 1%. Most of the adverse reactions leading to discontinuation were related to the gastrointestinal tract, e.g., nausea, vomiting, diarrhea, or abdominal pain. [see Clinical Studies (14.2)]

Adults

Multiple-dose regimens: Overall, the most common treatment-related adverse reactions in adult patients receiving multiple-dose regimens of ZITHROMAX were related to the gastrointestinal system with diarrhea/loose stools (4 to 5%), nausea (3%), and abdominal pain (2 to 3%) being the most frequently reported.

No other adverse reactions occurred in patients on the multiple-dose regimens of ZITHROMAX with a frequency greater than 1%. Adverse reactions that occurred with a frequency of 1% or less included the following:

Cardiovascular: Palpitations, chest pain.

Gastrointestinal: Dyspepsia, flatulence, vomiting, melena, and cholestatic jaundice.

Genitourinary: Monilia, vaginitis, and nephritis.

Nervous System: Dizziness, headache, vertigo, and somnolence.

General: Fatigue.

Allergic: Rash, pruritus, photosensitivity, and angioedema.

Single 1-gram dose regimen:

Overall, the most common adverse reactions in patients receiving a single-dose regimen of 1 gram of ZITHROMAX were related to the gastrointestinal system and were more frequently reported than in patients receiving the multiple-dose regimen.

Adverse reactions that occurred in patients on the single 1-gram dosing regimen of ZITHROMAX with a frequency of 1% or greater included diarrhea/loose stools (7%), nausea (5%), abdominal pain (5%), vomiting (2%), dyspepsia (1%), and vaginitis (1%).

Single 2-gram dose regimen:

Overall, the most common adverse reactions in patients receiving a single 2-gram dose of ZITHROMAX were related to the gastrointestinal system. Adverse reactions that occurred in patients in this study with a frequency of 1% or greater included nausea (18%), diarrhea/loose stools (14%), vomiting (7%), abdominal pain (7%), vaginitis (2%), dyspepsia (1%), and dizziness (1%). The majority of these complaints were mild in nature.

Pediatric Patients

Single and Multiple-dose regimens: The types of adverse reactions in pediatric patients were comparable to those seen in adults, with different incidence rates for the dosage regimens recommended in pediatric patients.

Acute Otitis Media: For the recommended total dosage regimen of 30 mg/kg, the most frequent adverse reactions (≥1%) attributed to treatment were diarrhea, abdominal pain, vomiting, nausea, and rash. [see Dosage and Administration (2) and Clinical Studies (14.2)]

The incidence, based on dosing regimen, is described in the table below:

Dosage Regimen | Diarrhea % | Abdominal Pain % | Vomiting % | Nausea % | Rash %
1-day | 4.3% | 1.4% | 4.9% | 1.0% | 1.0%
3-day | 2.6% | 1.7% | 2.3% | 0.4% | 0.6%
5-day | 1.8% | 1.2% | 1.1% | 0.5% | 0.4%

Community-Acquired Pneumonia: For the recommended dosage regimen of 10 mg/kg on Day 1 followed by 5 mg/kg on Days 2–5, the most frequent adverse reactions attributed to treatment were diarrhea/loose stools, abdominal pain, vomiting, nausea, and rash.

The incidence is described in the table below:

Dosage Regimen | Diarrhea/Loose stools % | Abdominal Pain % | Vomiting % | Nausea % | Rash %
5-day | 5.8% | 1.9% | 1.9% | 1.9% | 1.6%

Pharyngitis/Tonsillitis: For the recommended dosage regimen of 12 mg/kg on Days 1–5, the most frequent adverse reactions attributed to treatment were diarrhea, vomiting, abdominal pain, nausea, and headache.

The incidence is described in the table below:

Dosage Regimen | Diarrhea % | Abdominal Pain % | Vomiting % | Nausea % | Rash % | Headache %
5-day | 5.4% | 3.4% | 5.6% | 1.8% | 0.7% | 1.1%

With any of the treatment regimens, no other adverse reactions occurred in pediatric patients treated with ZITHROMAX with a frequency greater than 1%. Adverse reactions that occurred with a frequency of 1% or less included the following:

Cardiovascular: Chest pain.

Gastrointestinal: Dyspepsia, constipation, anorexia, enteritis, flatulence, gastritis, jaundice, loose stools, and oral moniliasis.

Hematologic and Lymphatic: Anemia and leukopenia.

Nervous System: Headache (otitis media dosage), hyperkinesia, dizziness, agitation, nervousness, and insomnia.

General: Fever, face edema, fatigue, fungal infection, malaise, and pain.

Allergic: Rash and allergic reaction.

Respiratory: Cough, pharyngitis, pleural effusion, and rhinitis.

Skin and Appendages: Eczema, fungal dermatitis, pruritus, sweating, urticaria, and vesiculobullous rash.

Special Senses: Conjunctivitis.

6.2 Postmarketing Experience

The following adverse reactions have been identified during post-approval use of azithromycin. Because these reactions are reported voluntarily from a population of uncertain size, it is not always possible to reliably estimate their frequency or establish a causal relationship to drug exposure.

Adverse reactions reported with azithromycin during the postmarketing period in adult and/or pediatric patients for which a causal relationship may not be established include:

Allergic: Arthralgia, edema, urticaria, and angioedema.

Cardiovascular: Arrhythmias including ventricular tachycardia and hypotension. There have been reports of QT prolongation, torsades de pointes, and cardiovascular death.

Gastrointestinal: Anorexia, constipation, dyspepsia, flatulence, vomiting/diarrhea, pseudomembranous colitis, pancreatitis, oral candidiasis, pyloric stenosis, and reports of tongue discoloration.

General: Asthenia, paresthesia, fatigue, malaise, and anaphylaxis.

Genitourinary: Interstitial nephritis and acute renal failure and vaginitis.

Hematopoietic: Thrombocytopenia.

Liver/Biliary: Abnormal liver function, hepatitis, cholestatic jaundice, hepatic necrosis, and hepatic failure. [see Warnings and Precautions (5.2)]

Nervous System: Convulsions, dizziness/vertigo, headache, somnolence, hyperactivity, nervousness, agitation, and syncope.

Psychiatric: Aggressive reaction and anxiety.

Skin/Appendages: Pruritus serious skin reactions including erythema multiforme, AGEP, Stevens-Johnson Syndrome, toxic epidermal necrolysis, and DRESS.

Special Senses: Hearing disturbances including hearing loss, deafness and/or tinnitus, and reports of taste/smell perversion and/or loss.

6.3 Laboratory Abnormalities

Adults:

Clinically significant abnormalities (irrespective of drug relationship) occurring during the clinical trials were reported as follows: with an incidence of greater than 1%: decreased hemoglobin, hematocrit, lymphocytes, neutrophils, and blood glucose; elevated serum creatine phosphokinase, potassium, ALT, GGT, AST, BUN, creatinine, blood glucose, platelet count, lymphocytes, neutrophils, and eosinophils; with an incidence of less than 1%: leukopenia, neutropenia, decreased sodium, potassium, platelet count, elevated monocytes, basophils, bicarbonate, serum alkaline phosphatase, bilirubin, LDH, and phosphate. The majority of subjects with elevated serum creatinine also had abnormal values at baseline. When follow-up was provided, changes in laboratory tests appeared to be reversible.

In multiple-dose clinical trials involving more than 5000 patients, four patients discontinued therapy because of treatment-related liver enzyme abnormalities and one because of a renal function abnormality.

Pediatric Patients:

One, Three, and Five-Day Regimens

Laboratory data collected from comparative clinical trials employing two 3-day regimens (30 mg/kg or 60 mg/kg in divided doses over 3 days), or two 5-day regimens (30 mg/kg or 60 mg/kg in divided doses over 5 days) were similar for regimens of azithromycin and all comparators combined, with most clinically significant laboratory abnormalities occurring at incidences of 1–5%. Laboratory data for patients receiving 30 mg/kg as a single dose were collected in one single center trial. In that trial, an absolute neutrophil count between 500–1500 cells/mm^3 was observed in 10/64 patients receiving 30 mg/kg as a single dose, 9/62 patients receiving 30 mg/kg given over 3 days, and 8/63 comparator patients. No patient had an absolute neutrophil count <500 cells/mm^3.

In multiple-dose clinical trials involving approximately 4700 pediatric patients, no patients discontinued therapy because of treatment-related laboratory abnormalities.

7 DRUG INTERACTIONS

7.1 Nelfinavir

Co-administration of nelfinavir at steady-state with a single oral dose of azithromycin resulted in increased azithromycin serum concentrations. Although a dose adjustment of azithromycin is not recommended when administered in combination with nelfinavir, close monitoring for known adverse reactions of azithromycin, such as liver enzyme abnormalities and hearing impairment, is warranted. [see Adverse Reactions (6)]

7.2 Warfarin

Spontaneous postmarketing reports suggest that concomitant administration of azithromycin may potentiate the effects of oral anticoagulants such as warfarin, although the prothrombin time was not affected in the dedicated drug interaction study with azithromycin and warfarin. Prothrombin times should be carefully monitored while patients are receiving azithromycin and oral anticoagulants concomitantly.

7.3 Potential Drug-Drug Interaction with Macrolides

Interactions with digoxin, colchicine or phenytoin have not been reported in clinical trials with azithromycin. No specific drug interaction studies have been performed to evaluate potential drug-drug interaction. However, drug interactions have been observed with other macrolide products. Until further data are developed regarding drug interactions when digoxin, colchicine or phenytoin are used with azithromycin careful monitoring of patients is advised.

8 USE IN SPECIFIC POPULATIONS

8.1 Pregnancy

Risk Summary

Available data from published literature and postmarketing experience over several decades with azithromycin use in pregnant women have not identified any drug-associated risks for major birth defects, miscarriage, or adverse maternal or fetal outcomes (see Data). Developmental toxicity studies with azithromycin in rats, mice, and rabbits showed no drug-induced fetal malformations at doses up to 4, 2, and 2 times, respectively, an adult human daily dose of 500 mg based on body surface area. Decreased viability and delayed development were observed in the offspring of pregnant rats administered azithromycin from day 6 of pregnancy through weaning at a dose equivalent to 4 times an adult human daily dose of 500 mg based on body surface area (see Data).

The estimated background risk of major birth defects and miscarriage for the indicated populations is unknown. All pregnancies have a background risk of birth defect, loss, or other adverse outcomes. In the U.S. general population, the estimated background risk of major birth defects and miscarriage in clinically recognized pregnancies is 2 to 4% and 15 to 20%, respectively.

Data

Human Data

Available data from published observational studies, case series, and case reports over several decades do not suggest an increased risk for major birth defects, miscarriage, or adverse maternal or fetal outcomes with azithromycin use in pregnant women. Limitations of these data include the lack of randomization and inability to control for confounders such as underlying maternal disease and maternal use of concomitant medications.

Animal Data

Azithromycin administered during the period of organogenesis did not cause fetal malformations in rats and mice at oral doses up to 200 mg/kg/day (moderately maternally toxic). Based on body surface area, this dose is approximately 4 (rats) and 2 (mice) times an adult human daily dose of 500 mg. In rabbits administered azithromycin at oral doses of 10, 20, and 40 mg/kg/day during organogenesis, reduced maternal body weight and food consumption were observed in all groups; no evidence of fetotoxicity or teratogenicity was observed at these doses, the highest of which is estimated to be 2 times an adult human daily dose of 500 mg based on body surface area.

In a pre- and postnatal development study, azithromycin was administered orally to pregnant rats from day 6 of pregnancy until weaning at doses of 50 or 200 mg/kg/day. Maternal toxicity (reduced food consumption and body weight gain; increased stress at parturition) was observed at the higher dose. Effects in the offspring were noted at 200 mg/kg/day during the postnatal development period (decreased viability, delayed developmental landmarks). These effects were not observed in a pre- and postnatal rat study when up to 200 mg/kg/day of azithromycin was given orally beginning on day 15 of pregnancy until weaning.

8.2 Lactation

Risk Summary

Azithromycin is present in human milk (see Data). Non-serious adverse reactions have been reported in breastfed infants after maternal administration of azithromycin (see Clinical Considerations). There are no available data on the effects of azithromycin on milk production. The developmental and health benefits of breastfeeding should be considered along with the mother's clinical need for ZITHROMAX and any potential adverse effects on the breastfed infant from ZITHROMAX or from the underlying maternal condition.

Clinical Considerations

Advise women to monitor the breastfed infant for diarrhea, vomiting, or rash.

Data

Azithromycin breastmilk concentrations were measured in 20 women after receiving a single 2 g oral dose of azithromycin during labor. Breastmilk samples collected on days 3 and 6 postpartum as well as 2 and 4 weeks postpartum revealed the presence of azithromycin in breastmilk up to 4 weeks after dosing. In another study, a single dose of azithromycin 500 mg was administered intravenously to 8 women prior to incision for cesarean section. Breastmilk (colostrum) samples obtained between 12 and 48 hours after dosing revealed that azithromycin persisted in breastmilk up to 48 hours.

8.4 Pediatric Use

[see Clinical Pharmacology (12.3), Indications and Usage (1.2), and Dosage and Administration (2.2)]

Safety and effectiveness in the treatment of pediatric patients with acute otitis media, acute bacterial sinusitis and community-acquired pneumonia under 6 months of age have not been established. Use of ZITHROMAX for the treatment of acute bacterial sinusitis and community-acquired pneumonia in pediatric patients (6 months of age or greater) is supported by adequate and well-controlled trials in adults.

Pharyngitis/Tonsillitis: Safety and effectiveness in the treatment of pediatric patients with pharyngitis/tonsillitis under 2 years of age have not been established.

8.5 Geriatric Use

In multiple-dose clinical trials of oral azithromycin, 9% of patients were at least 65 years of age (458/4949) and 3% of patients (144/4949) were at least 75 years of age. No overall differences in safety or effectiveness were observed between these subjects and younger subjects, and other reported clinical experience has not identified differences in response between the elderly and younger patients, but greater sensitivity of some older individuals cannot be ruled out.

Elderly patients may be more susceptible to development of torsades de pointes arrhythmias than younger patients. [see Warnings and Precautions (5.4)]

10 OVERDOSAGE

Adverse reactions experienced at higher than recommended doses were similar to those seen at normal doses particularly nausea, diarrhea, and vomiting. In the event of overdosage, general symptomatic and supportive measures are indicated as required.

11 DESCRIPTION

ZITHROMAX (azithromycin tablets and azithromycin for oral suspension) contain the active ingredient azithromycin, a macrolide antibacterial drug, for oral administration. Azithromycin has the chemical name (2R,3S,4R,5R,8R,10R,11R,12S,13S,14R)-13-[(2,6-dideoxy-3-C-methyl-3-O-methyl-α-L-ribo-hexopyranosyl) oxy]-2-ethyl-3,4,10-trihydroxy-3,5,6,8,10,12,14-heptamethyl-11-[[3,4,6-trideoxy-3-(dimethylamino)-β-D-xylo-hexopyranosyl]oxy]-1-oxa-6-azacyclopentadecan-15-one. Azithromycin is derived from erythromycin; however, it differs chemically from erythromycin in that a methyl-substituted nitrogen atom is incorporated into the lactone ring. Its molecular formula is C38H72N2O12, and its molecular weight is 749.00. Azithromycin has the following structural formula:

Azithromycin, as the dihydrate, is a white crystalline powder with a molecular formula of C38H72N2O12∙2H2O and a molecular weight of 785.0.

ZITHROMAX is supplied as tablets containing azithromycin dihydrate equivalent to either 250 mg or 500 mg azithromycin and the following inactive ingredients: dibasic calcium phosphate anhydrous, pregelatinized starch, sodium croscarmellose, magnesium stearate, sodium lauryl sulfate, hypromellose, lactose, titanium dioxide, triacetin, and D&C Red #30 aluminum lake.

ZITHROMAX for oral suspension is supplied in bottles containing azithromycin dihydrate powder equivalent to 300 mg, 600 mg, 900 mg, or 1200 mg azithromycin per bottle and the following inactive ingredients: sucrose; sodium phosphate, tribasic, anhydrous; hydroxypropyl cellulose; xanthan gum; FD&C Red #40; and spray dried artificial cherry, creme de vanilla, and banana flavors. After constitution, each 5 mL of suspension contains 100 mg or 200 mg of azithromycin.

12 CLINICAL PHARMACOLOGY

12.1 Mechanism of Action

Azithromycin is a macrolide antibacterial drug. [see Microbiology (12.4)]

12.2 Pharmacodynamics

Based on animal models of infection, the antibacterial activity of azithromycin appears to correlate with the ratio of area under the concentration-time curve to minimum inhibitory concentration (AUC/MIC) for certain pathogens (S. pneumoniae and S. aureus). The principal pharmacokinetic/pharmacodynamic parameter best associated with clinical and microbiological cure has not been elucidated in clinical trials with azithromycin.

Cardiac Electrophysiology

QTc interval prolongation was studied in a randomized, placebo-controlled parallel trial in 116 healthy subjects who received either chloroquine (1000 mg) alone or in combination with oral azithromycin (500 mg, 1000 mg, and 1500 mg once daily). Co-administration of azithromycin increased the QTc interval in a dose- and concentration- dependent manner. In comparison to chloroquine alone, the maximum mean (95% upper confidence bound) increases in QTcF were 5 (10) ms, 7 (12) ms and 9 (14) ms with the co-administration of 500 mg, 1000 mg and 1500 mg azithromycin, respectively.

12.3 Pharmacokinetics

Following oral administration of a single 500 mg dose (two 250 mg tablets) to 36 fasted healthy male volunteers, the mean (SD) pharmacokinetic parameters were AUC0–72=4.3 (1.2) mcg∙hr/mL; Cmax=0.5 (0.2) mcg/mL; Tmax=2.2 (0.9) hours. Two azithromycin 250 mg tablets are bioequivalent to a single 500 mg tablet.

In a two-way crossover study, 12 adult healthy volunteers (6 males, 6 females) received 1500 mg of azithromycin administered in single daily doses over either 5 days (two 250 mg tablets on day 1, followed by one 250 mg tablet on days 2–5) or 3 days (500 mg per day for days 1–3). Due to limited serum samples on day 2 (3-day regimen) and days 2–4 (5-day regimen), the serum concentration-time profile of each subject was fit to a 3-compartment model and the AUC0–∞ for the fitted concentration profile was comparable between the 5-day and 3-day regimens.

 | 3-Day Regimen |  | 5-Day Regimen
Pharmacokinetic Parameter [mean (SD)] | Day 1 | Day 3 | Day 1 | Day 5
Cmax (serum, mcg/mL) | 0.44 (0.22) | 0.54 (0.25) | 0.43 (0.20) | 0.24 (0.06)
Serum AUC0–∞ (mcg∙hr/mL) | 17.4 (6.2) [Total AUC for the entire 3-day and 5-day regimens.] |  | 14.9 (3.1)
Serum T1/2 | 71.8 hr |  | 68.9 hr

Absorption

The absolute bioavailability of azithromycin 250 mg capsules is 38%.

In a two-way crossover study in which 12 healthy subjects received a single 500 mg dose of azithromycin (two 250 mg tablets) with or without a high fat meal, food was shown to increase Cmax by 23% but had no effect on AUC.

When azithromycin oral suspension was administered with food to 28 adult healthy male subjects, Cmax increased by 56% and AUC was unchanged.

Distribution

The serum protein binding of azithromycin is variable in the concentration range approximating human exposure, decreasing from 51% at 0.02 mcg/mL to 7% at 2 mcg/mL.

The antibacterial activity of azithromycin is pH related and appears to be reduced with decreasing pH, However, the extensive distribution of drug to tissues may be relevant to clinical activity.

Azithromycin has been shown to penetrate into human tissues, including skin, lung, tonsil, and cervix. Extensive tissue distribution was confirmed by examination of additional tissues and fluids (bone, ejaculum, prostate, ovary, uterus, salpinx, stomach, liver, and gallbladder). As there are no data from adequate and well-controlled studies of azithromycin treatment of infections in these additional body sites, the clinical significance of these tissue concentration data is unknown.

Following a regimen of 500 mg on the first day and 250 mg daily for 4 days, very low concentrations were noted in cerebrospinal fluid (less than 0.01 mcg/mL) in the presence of noninflamed meninges.

Metabolism

In vitro and in vivo studies to assess the metabolism of azithromycin have not been performed.

Elimination

Plasma concentrations of azithromycin following single 500 mg oral and IV doses declined in a polyphasic pattern resulting in a mean apparent plasma clearance of 630 mL/min and terminal elimination half-life of 68 hr. The prolonged terminal half-life is thought to be due to extensive uptake and subsequent release of drug from tissues. Biliary excretion of azithromycin, predominantly as unchanged drug, is a major route of elimination. Over the course of a week, approximately 6% of the administered dose appears as unchanged drug in urine.

Specific Populations

Patients with Renal Impairment

Azithromycin pharmacokinetics was investigated in 42 adults (21 to 85 years of age) with varying degrees of renal impairment. Following the oral administration of a single 1.0 g dose of azithromycin (4 × 250 mg capsules), mean Cmax and AUC0–120 increased by 5.1% and 4.2%, respectively, in subjects with mild to moderate renal impairment (GFR 10 to 80 mL/min) compared to subjects with normal renal function (GFR >80 mL/min). The mean Cmax and AUC0–120 increased 61% and 35%, respectively, in subjects with severe renal impairment (GFR <10 mL/min) compared to subjects with normal renal function (GFR >80 mL/min).

Patients with Hepatic Impairment

The pharmacokinetics of azithromycin in subjects with hepatic impairment has not been established.

Male and Female Patients

There are no significant differences in the disposition of azithromycin between male and female subjects. No dosage adjustment is recommended based on gender.

Geriatric Patients

Pharmacokinetic parameters in older volunteers (65 to 85 years old) were similar to those in young adults (18 to 40 years old) for the 5-day therapeutic regimen. Dosage adjustment does not appear to be necessary for older patients with normal renal and hepatic function receiving treatment with this dosage regimen. [see Geriatric Use (8.5)]

Pediatric Patients

In two clinical studies, azithromycin for oral suspension was dosed at 10 mg/kg on day 1, followed by 5 mg/kg on days 2 through 5 in two groups of pediatric patients (aged 1–5 years and 5–15 years, respectively). The mean pharmacokinetic parameters on day 5 were Cmax=0.216 mcg/mL, Tmax=1.9 hr, and AUC0–24=1.822 mcg∙hr/mL for the 1 to 5-year-old group and were Cmax=0.383 mcg/mL, Tmax=2.4 hr, and AUC0–24=3.109 mcg∙hr/mL for the 5 to 15-year-old group.

In another study, 33 pediatric patients received doses of 12 mg/kg/day (maximum daily dose 500 mg) for 5 days, of whom 31 patients were evaluated for azithromycin pharmacokinetics following a low fat breakfast. In this study, azithromycin concentrations were determined over a 24 hr period following the last daily dose. Patients weighing above 41.7 kg received the maximum adult daily dose of 500 mg. Seventeen patients (weighing 41.7 kg or less) received a total dose of 60 mg/kg. The following table shows pharmacokinetic data in the subset of pediatric patients who received a total dose of 60 mg/kg.

Pharmacokinetic Parameter [mean (SD)] | 5-Day Regimen (12 mg/kg for 5 days)
N | 17
Cmax (mcg/mL) | 0.5 (0.4)
Tmax (hr) | 2.2 (0.8)
AUC0–24(mcg∙hr/mL) | 3.9 (1.9)

Single dose pharmacokinetics of azithromycin in pediatric patients given doses of 30 mg/kg have not been studied. [see Dosage and Administration (2)]

Drug Interaction Studies

Drug interaction studies were performed with azithromycin and other drugs likely to be co-administered. The effects of co-administration of azithromycin on the pharmacokinetics of other drugs are shown in Table 1 and the effects of other drugs on the pharmacokinetics of azithromycin are shown in Table 2.

Co-administration of azithromycin at therapeutic doses had a modest effect on the pharmacokinetics of the drugs listed in Table 1. No dosage adjustment of drugs listed in Table 1 is recommended when co-administered with azithromycin.

Co-administration of azithromycin with efavirenz or fluconazole had a modest effect on the pharmacokinetics of azithromycin. Nelfinavir significantly increased the Cmax and AUC of azithromycin. No dosage adjustment of azithromycin is recommended when administered with drugs listed in Table 2. [see Drug Interactions (7.3)]

Table 1. Drug Interactions: Pharmacokinetic Parameters for Co-administered Drugs in the Presence of Azithromycin
Co-administered Drug | Dose of Co-administered Drug | Dose of Azithromycin | n | Ratio (with/without azithromycin) of Co-administered Drug Pharmacokinetic Parameters (90% CI); No Effect = 1.00
Co-administered Drug | Dose of Co-administered Drug | Dose of Azithromycin | n | Mean Cmax | Mean AUC
Atorvastatin | 10 mg/day for 8 days | 500 mg/day orally on days 6–8 | 12 | 0.83 (0.63 to 1.08) | 1.01 (0.81 to 1.25)
Carbamazepine | 200 mg/day for 2 days, then 200 mg twice a day for 18 days | 500 mg/day orally for days 16–18 | 7 | 0.97 (0.88 to 1.06) | 0.96 (0.88 to 1.06)
Cetirizine | 20 mg/day for 11 days | 500 mg orally on day 7, then 250 mg/day on days 8–11 | 14 | 1.03 (0.93 to 1.14) | 1.02 (0.92 to 1.13)
Didanosine | 200 mg orally twice a day for 21 days | 1200 mg/day orally on days 8–21 | 6 | 1.44 (0.85 to 2.43) | 1.14 (0.83 to 1.57)
Efavirenz | 400 mg/day for 7 days | 600 mg orally on day 7 | 14 | 1.04 [- 90% Confidence interval not reported] | 0.95
Fluconazole | 200 mg orally single dose | 1200 mg orally single dose | 18 | 1.04 (0.98 to 1.11) | 1.01 (0.97 to 1.05)
Indinavir | 800 mg three times a day for 5 days | 1200 mg orally on day 5 | 18 | 0.96 (0.86 to 1.08) | 0.90 (0.81 to 1.00)
Midazolam | 15 mg orally on day 3 | 500 mg/day orally for 3 days | 12 | 1.27 (0.89 to 1.81) | 1.26 (1.01 to 1.56)
Nelfinavir | 750 mg three times a day for 11 days | 1,200 mg orally on day 9 | 14 | 0.90 (0.81 to 1.01) | 0.85 (0.78 to 0.93)
Sildenafil | 100 mg on days 1 and 4 | 500 mg/day orally for 3 days | 12 | 1.16 (0.86 to 1.57) | 0.92 (0.75 to 1.12)
Theophylline | 4 mg/kg IV on days 1, 11, 25 | 500 mg orally on day 7, 250 mg/day on days 8–11 | 10 | 1.19 (1.02 to 1.40) | 1.02 (0.86 to 1.22)
Theophylline | 300 mg orally twice a day for 15 days | 500 mg orally on day 6, then 250 mg/day on days 7–10 | 8 | 1.09 (0.92 to 1.29) | 1.08 (0.89 to 1.31)
Triazolam | 0.125 mg on day 2 | 500 mg orally on day 1, then 250 mg/day on day 2 | 12 | 1.06 | 1.02
Trimethoprim/ Sulfamethoxazole | 160 mg/800 mg/day orally for 7 days | 1200 mg orally on day 7 | 12 | 0.85 (0.75 to 0.97)/0.90 (0.78 to 1.03) | 0.87 (0.80 to 0.95/0.96 (0.88 to 1.03)
Zidovudine | 500 mg/day orally for 21 days | 600 mg/day orally for 14 days | 5 | 1.12 (0.42 to 3.02) | 0.94 (0.52 to 1.70)
Zidovudine | 500 mg/day orally for 21 days | 1200 mg/day orally for 14 days | 4 | 1.31 (0.43 to 3.97) | 1.30 (0.69 to 2.43)

Table 2. Drug Interactions: Pharmacokinetic Parameters for Azithromycin in the Presence of Co-administered Drugs. [see Drug Interactions (7)]
Co-administered Drug | Dose of Co-administered Drug | Dose of Azithromycin | n | Ratio (with/without co-administered drug) of Azithromycin Pharmacokinetic Parameters (90% CI); No Effect = 1.00
Co-administered Drug | Dose of Co-administered Drug | Dose of Azithromycin | n | Mean Cmax | Mean AUC
Efavirenz | 400 mg/day for 7 days | 600 mg orally on day 7 | 14 | 1.22 (1.04 to 1.42) | 0.92 [- 90% Confidence interval not reported]
Fluconazole | 200 mg orally single dose | 1,200 mg orally single dose | 18 | 0.82 (0.66 to 1.02) | 1.07 (0.94 to 1.22)
Nelfinavir | 750 mg three times a day for 11 days | 1,200 mg orally on day 9 | 14 | 2.36 (1.77 to 3.15) | 2.12 (1.80 to 2.50)

12.4 Microbiology

Mechanism of Action

Azithromycin acts by binding to the 23S rRNA of the 50S ribosomal subunit of susceptible microorganisms inhibiting bacterial protein synthesis and impeding the assembly of the 50S ribosomal subunit.

Resistance

Azithromycin demonstrates cross resistance with erythromycin. The most frequently encountered mechanism of resistance to azithromycin is modification of the 23S rRNA target, most often by methylation. Ribosomal modifications can determine cross resistance to other macrolides, lincosamides, and streptogramin B (MLSB phenotype).

Antimicrobial Activity

Azithromycin has been shown to be active against most isolates of the following microorganisms, both in vitro and in clinical infections. [see Indications and Usage (1)]

Gram-Positive Bacteria

Staphylococcus aureus
Streptococcus agalactiae
Streptococcus pneumoniae
Streptococcus pyogenes

Gram-Negative Bacteria

Haemophilus ducreyi
Haemophilus influenzae
Moraxella catarrhalis
Neisseria gonorrhoeae

Other Bacteria

Chlamydophila pneumoniae
Chlamydia trachomatis
Mycoplasma pneumoniae

The following in vitro data are available, but their clinical significance is unknown. At least 90 percent of the following bacteria exhibit an in vitro minimum inhibitory concentration (MIC) less than or equal to the susceptible breakpoint for azithromycin against isolates of similar genus or organism group. However, the efficacy of azithromycin in treating clinical infections caused by these bacteria has not been established in adequate and well-controlled clinical trials.

Gram-Positive Bacteria

Beta-hemolytic streptococci (Groups C, F, G)
Viridans group streptococci

Gram-Negative Bacteria

Bordetella pertussis
Legionella pneumophila

Anaerobic Bacteria

Prevotella bivia
Peptostreptococcus species

Other Bacteria

Ureaplasma urealyticum

Susceptibility Testing

For specific information regarding susceptibility test interpretive criteria and associated test methods and quality control standards recognized by FDA for this drug, please see: https://www.fda.gov/STIC.

13 NONCLINICAL TOXICOLOGY

13.1 Carcinogenesis, Mutagenesis, Impairment of Fertility

Long-term studies in animals have not been performed to evaluate carcinogenic potential. Azithromycin has shown no mutagenic potential in standard laboratory tests: mouse lymphoma assay, human lymphocyte clastogenic assay, and mouse bone marrow clastogenic assay. In fertility studies conducted in male and female rats, oral administration of azithromycin for 64 to 66 days (males) or 15 days (females) prior to and during cohabitation resulted in decreased pregnancy rate at 20 and 30 mg/kg/day when both males and females were treated with azithromycin. This minimal effect on pregnancy rate (approximately 12% reduction compared to concurrent controls) did not become more pronounced when the dose was increased from 20 to 30 mg/kg/day (approximately 0.4 to 0.6 times the adult daily dose of 500 mg based on body surface area) and it was not observed when only one animal in the mated pair was treated. There were no effects on any other reproductive parameters, and there were no effects on fertility at 10 mg/kg/day. The relevance of these findings to patients being treated with azithromycin at the doses and durations recommended in the prescribing information is uncertain.

13.2 Animal Toxicology and/or Pharmacology

Phospholipidosis (intracellular phospholipid accumulation) has been observed in some tissues of mice, rats, and dogs given multiple doses of azithromycin. It has been demonstrated in numerous organ systems (e.g., eye, dorsal root ganglia, liver, gallbladder, kidney, spleen, and/or pancreas) in dogs and rats treated with azithromycin at doses which, expressed on the basis of body surface area, are similar to or less than the highest recommended adult human dose. This effect has been shown to be reversible after cessation of azithromycin treatment. Based on the pharmacokinetic data, phospholipidosis has been seen in the rat (50 mg/kg/day dose) at the observed maximal plasma concentration of 1.3 mcg/mL (1.6 times the observed Cmax of 0.821 mcg/mL at the adult dose of 2 g). Similarly, it has been shown in the dog (10 mg/kg/day dose) at the observed maximal serum concentration of 1 mcg/mL (1.2 times the observed Cmax of 0.821 mcg/mL at the adult dose of 2 g). Phospholipidosis was also observed in neonatal rats dosed for 18 days at 30 mg/kg/day, which is less than the pediatric dose of 60 mg/kg based on the surface area. It was not observed in neonatal rats treated for 10 days at 40 mg/kg/day with mean maximal serum concentrations of 1.86 mcg/mL, approximately 1.5 times the Cmax of 1.27 mcg/mL at the pediatric dose. Phospholipidosis has been observed in neonatal dogs (10 mg/kg/day) at maximum mean whole blood concentrations of 3.54 mcg/mL, approximately 3 times the pediatric dose Cmax. The significance of these findings for animals and for humans is unknown.

14 CLINICAL STUDIES

14.1 Adult Patients

Acute Bacterial Exacerbations of Chronic Bronchitis

In a randomized, double-blind controlled clinical trial of acute exacerbation of chronic bronchitis (AECB), azithromycin (500 mg once daily for 3 days) was compared with clarithromycin (500 mg twice daily for 10 days). The primary endpoint of this trial was the clinical cure rate at Days 21– 24. For the 304 patients analyzed in the modified intent-to-treat analysis at the Days 21–24 visit, the clinical cure rate for 3 days of azithromycin was 85% (125/147) compared to 82% (129/157) for 10 days of clarithromycin.

The following outcomes were the clinical cure rates at the Days 21–24 visit for the bacteriologically evaluable patients by pathogen:

Pathogen | Azithromycin (3 Days) | Clarithromycin (10 Days)
S. pneumoniae | 29/32 (91%) | 21/27 (78%)
H. influenzae | 12/14 (86%) | 14/16 (88%)
M. catarrhalis | 11/12 (92%) | 12/15 (80%)

Acute Bacterial Sinusitis

In a randomized, double-blind, double-dummy controlled clinical trial of acute bacterial sinusitis, azithromycin (500 mg once daily for 3 days) was compared with amoxicillin/clavulanate (500/125 mg three times a day for 10 days). Clinical response assessments were made at Day 10 and Day 28. The primary endpoint of this trial was prospectively defined as the clinical cure rate at Day 28. For the 594 patients analyzed in the modified intent to treat analysis at the Day 10 visit, the clinical cure rate for 3 days of azithromycin was 88% (268/303) compared to 85% (248/291) for 10 days of amoxicillin/clavulanate. For the 586 patients analyzed in the modified intent to treat analysis at the Day 28 visit, the clinical cure rate for 3 days of azithromycin was 71.5% (213/298) compared to 71.5% (206/288), with a 97.5% confidence interval of –8.4 to 8.3, for 10 days of amoxicillin/clavulanate.

In an open label, non-comparative study requiring baseline transantral sinus punctures, the following outcomes were the clinical success rates at the Day 7 and Day 28 visits for the modified intent to treat patients administered 500 mg of azithromycin once daily for 3 days with the following pathogens:

Clinical Success Rates of Azithromycin (500 mg per day for 3 Days)
Pathogen | Day 7 | Day28
S. pneumoniae | 23/26 (88%) | 21/25 (84%)
H. influenzae | 28/32 (87%) | 24/32 (75%)
M. catarrhalis | 14/15 (93%) | 13/15 (87%)

14.2 Pediatric Patients

From the perspective of evaluating pediatric clinical trials, Days 11–14 were considered on-therapy evaluations because of the extended half-life of azithromycin. Days 11–14 data are provided for clinical guidance. Days 24–32 evaluations were considered the primary test of cure endpoint.

Pharyngitis/Tonsillitis

In three double-blind controlled studies, conducted in the United States, azithromycin (12 mg/kg once a day for 5 days) was compared to penicillin V (250 mg three times a day for 10 days) in the treatment of pharyngitis due to documented Group A β-hemolytic streptococci (GABHS or S. pyogenes). Azithromycin was clinically and microbiologically statistically superior to penicillin at Day 14 and Day 30 with the following clinical success (i.e., cure and improvement) and bacteriologic efficacy rates (for the combined evaluable patient with documented GABHS):

Three U.S. Streptococcal Pharyngitis Studies Azithromycin vs. Penicillin V EFFICACY RESULTS
 | Day 14 | Day 30
Bacteriologic Eradication:
Azithromycin | 323/340 (95%) | 255/330 (77%)
Penicillin V | 242/332 (73%) | 206/325 (63%)
Clinical Success (cure plus improvement):
Azithromycin | 336/343 (98%) | 310/330 (94%)
Penicillin V | 284/338 (84%) | 241/325 (74%)

Approximately 1% of azithromycin-susceptible S. pyogenes isolates were resistant to azithromycin following therapy.

Acute Otitis Media

Efficacy using azithromycin given over 5 days (10 mg/kg on Day 1 followed by 5 mg/kg on Days 2–5).

Trial 1

In a double-blind, controlled clinical study of acute otitis media performed in the United States, azithromycin (10 mg/kg on Day 1 followed by 5 mg/kg on Days 2–5) was compared to amoxicillin/clavulanate potassium (4:1). For the 553 patients who were evaluated for clinical efficacy, the clinical success rate (i.e., cure plus improvement) at the Day 11 visit was 88% for azithromycin and 88% for the control agent. For the 521 patients who were evaluated at the Day 30 visit, the clinical success rate was 73% for azithromycin and 71% for the control agent.

Trial 2

In a non-comparative clinical and microbiologic trial performed in the United States, where significant rates of beta-lactamase producing organisms (35%) were found, 131 patients were evaluable for clinical efficacy. The combined clinical success rate (i.e., cure and improvement) at the Day 11 visit was 84% for azithromycin. For the 122 patients who were evaluated at the Day 30 visit, the clinical success rate was 70% for azithromycin.

Microbiologic determinations were made at the pre-treatment visit. Microbiology was not reassessed at later visits. The following clinical success rates were obtained from the evaluable group:

Pathogen
 | Day 11 | Day 30
 | Azithromycin | Azithromycin
S. pneumoniae | 61/74 (82%) | 40/56 (71%)
H. influenzae | 43/54 (80%) | 30/47 (64%)
M. catarrhalis | 28/35 (80%) | 19/26 (73%)
S. pyogenes | 11/11 (100%) | 7/7 (100%)
Overall | 177/217 (82%) | 97/137 (73%)

Trial 3

In another controlled comparative clinical and microbiologic study of otitis media performed in the United States, azithromycin (10 mg/kg on Day 1 followed by 5 mg/kg on Days 2–5) was compared to amoxicillin/clavulanate potassium (4:1). This study utilized two of the same investigators as Protocol 2 (above), and these two investigators enrolled 90% of the patients in Protocol 3. For this reason, Protocol 3 was not considered to be an independent study. Significant rates of beta-lactamase producing organisms (20%) were found. Ninety-two (92) patients were evaluable for clinical and microbiologic efficacy. The combined clinical success rate (i.e., cure and improvement) of those patients with a baseline pathogen at the Day 11 visit was 88% for azithromycin vs. 100% for control; at the Day 30 visit, the clinical success rate was 82% for azithromycin vs. 80% for control.

Microbiologic determinations were made at the pre-treatment visit. Microbiology was not reassessed at later visits. At the Day 11 and Day 30 visits, the following clinical success rates were obtained from the evaluable group:

 | Day 11 |  | Day 30
Pathogen | Azithromycin | Control | Azithromycin | Control
S. pneumoniae | 25/29 (86%) | 26/26 (100%) | 22/28 (79%) | 18/22 (82%)
H. influenzae | 9/11 (82%) | 9/9 (100%) | 8/10 (80%) | 6/8 (75%)
M. catarrhalis | 7/7 (100%) | 5/5 (100%) | 5/5 (100%) | 2/3 (66%)
S. pyogenes | 2/2 (100%) | 5/5 (100%) | 2/2 (100%) | 4/4 (100%)
Overall | 43/49 (88%) | 45/45 (100%) | 37/45 (82%) | 30/37 (81%)

Efficacy using azithromycin given over 3 days (10 mg/kg/day).

Trial 4

In a double-blind, controlled, randomized clinical study of acute otitis media in pediatric patients from 6 months to 12 years of age, azithromycin (10 mg/kg per day for 3 days) was compared to amoxicillin/clavulanate potassium (7:1) in divided doses q12h for 10 days. Each patient received active drug and placebo matched for the comparator.

For the 366 patients who were evaluated for clinical efficacy at the Day 12 visit, the clinical success rate (i.e., cure plus improvement) was 83% for azithromycin and 88% for the control agent. For the 362 patients who were evaluated at the Days 24–28 visit, the clinical success rate was 74% for azithromycin and 69% for the control agent.

Efficacy using azithromycin 30 mg/kg given as a single dose

Trial 5

A double-blind, controlled, randomized trial was performed at nine clinical centers. Pediatric patients from 6 months to 12 years of age were randomized 1:1 to treatment with either azithromycin (given at 30 mg/kg as a single dose on Day 1) or amoxicillin/clavulanate potassium (7:1), divided q12h for 10 days. Each child received active drug, and placebo matched for the comparator.

Clinical response (Cure, Improvement, Failure) was evaluated at End of Therapy (Days 12–16) and Test of Cure (Days 28–32). Safety was evaluated throughout the trial for all treated subjects. For the 321 subjects who were evaluated at End of Treatment, the clinical success rate (cure plus improvement) was 87% for azithromycin, and 88% for the comparator. For the 305 subjects who were evaluated at Test of Cure, the clinical success rate was 75% for both azithromycin and the comparator.

Trial 6

In a non-comparative clinical and microbiological trial, 248 patients from 6 months to 12 years of age with documented acute otitis media were dosed with a single oral dose of azithromycin (30 mg/kg on Day 1).

For the 240 patients who were evaluable for clinical modified Intent-to-Treat (MITT) analysis, the clinical success rate (i.e., cure plus improvement) at Day 10 was 89% and for the 242 patients evaluable at Days 24–28, the clinical success rate (cure) was 85%.

Presumed Bacteriologic Eradication
 | Day 10 | Days 24–28
S. pneumoniae | 70/76 (92%) | 67/76 (88%)
H. influenzae | 30/42 (71%) | 28/44 (64%)
M. catarrhalis | 10/10 (100%) | 10/10 (100%)
Overall | 110/128 (86%) | 105/130 (81%)

16 HOW SUPPLIED/STORAGE AND HANDLING

ZITHROMAX is supplied in the following strengths and package configurations:

Tablet strength | Tablet Color/Shape | Tablet Markings | Package Size | NDC Code
250 mg (containing azithromycin dihydrate equivalent to 250 mg of azithromycin) | Pink modified capsular shaped, engraved, film-coated | Engraved with "PFIZER" on one side and "306" on the other | Bottles of 30 | NDC 0069-3060-30
250 mg (containing azithromycin dihydrate equivalent to 250 mg of azithromycin) | Pink modified capsular shaped, engraved, film-coated | Engraved with "PFIZER" on one side and "306" on the other | Boxes of 3 (Z-PAKS® of 6) | NDC 0069-3060-75
250 mg (containing azithromycin dihydrate equivalent to 250 mg of azithromycin) | Pink modified capsular shaped, engraved, film-coated | Engraved with "PFIZER" on one side and "306" on the other | Unit Dose package of 50 | NDC 0069-3060-86
250 mg (containing azithromycin dihydrate equivalent to 250 mg of azithromycin) | Pink modified capsular shaped, engraved, film-coated | Engraved with "Pfizer" on one side and "ZTM 250" on the other | Bottles of 30 | NDC 0069-4061-01
250 mg (containing azithromycin dihydrate equivalent to 250 mg of azithromycin) | Pink modified capsular shaped, engraved, film-coated | Engraved with "Pfizer" on one side and "ZTM 250" on the other | Boxes of 3 (Z-PAKS® of 6) | NDC 0069-4061-75
250 mg (containing azithromycin dihydrate equivalent to 250 mg of azithromycin) | Pink modified capsular shaped, engraved, film-coated | Engraved with "Pfizer" on one side and "ZTM 250" on the other | Unit Dose package of 50 | NDC 0069-4061-89
500 mg (containing azithromycin dihydrate equivalent to 500 mg of azithromycin) | Pink modified capsular shaped, engraved, film coated | Engraved with "Pfizer" on one side and "ZTM500" on the other | Bottles of 30 | NDC 0069-3070-30
500 mg (containing azithromycin dihydrate equivalent to 500 mg of azithromycin) | Pink modified capsular shaped, engraved, film coated | Engraved with "Pfizer" on one side and "ZTM500" on the other | Boxes of 3 (TRI-PAKS™ of 3 tablets) | NDC 0069-3070-75

ZITHROMAX tablets should be stored between 15° to 30°C (59° to 86°F).

ZITHROMAX for oral suspension after constitution contains a flavored suspension. ZITHROMAX for oral suspension is supplied to provide 100 mg/5 mL or 200 mg/5 mL suspension in bottles as follows:

Azithromycin contents per bottle | NDC
300 mg | 0069-3110-19
600 mg | 0069-3120-19
900 mg | 0069-3130-19
1200 mg | 0069-3140-19

[see Dosage and Administration (2)] for constitution instructions with each bottle type.

STORAGE AND HANDLING

Storage: Store dry powder below 30°C (86°F). Store constituted suspension between 5° to 30°C (41° to 86°F) and discard when full dosing is completed.

17 PATIENT COUNSELING INFORMATION

Advise the patient to read the FDA-approved patient labeling (Patient Information).

General Patient Counseling

ZITHROMAX tablets and oral suspension can be taken with or without food.

Patients should also be cautioned not to take aluminum- and magnesium-containing antacids and azithromycin simultaneously.

The patient should be directed to discontinue azithromycin immediately and contact a physician if any signs of an allergic reaction occur.

Direct parents or caregivers to contact their physician if vomiting and irritability with feeding occurs in the infant.

Patients should be counseled that antibacterial drugs including ZITHROMAX (azithromycin) should only be used to treat bacterial infections. They do not treat viral infections (e.g., the common cold). When ZITHROMAX (azithromycin) is prescribed to treat a bacterial infection, patients should be told that although it is common to feel better early in the course of the therapy, the medication should be taken exactly as directed. Skipping doses or not completing the full course of therapy may (1) decrease the effectiveness of the immediate treatment and (2) increase the likelihood that bacteria will develop resistance and will not be treatable by ZITHROMAX (azithromycin) or other antibacterial drugs in the future.

Diarrhea is a common problem caused by antibacterials which usually ends when the antibacterial is discontinued. Sometimes after starting treatment with antibacterials patients can develop watery and bloody stools (with or without stomach cramps and fever) even as late as two or more months after having taken the last dose of the antibacterial drug. If this occurs, patients should contact their physician as soon as possible.

Licensed from Pliva

This product's label may have been updated. For current full prescribing information, please visit www.pfizer.com.

LAB-0023-23.0

Patient Information

ZITHROMAX® (Zith-roe-maks)
(azithromycin)
Tablets

ZITHROMAX®
(azithromycin)
Oral Suspension

Read this Patient Information leaflet before you start taking ZITHROMAX and each time you get a refill. There may be new information. This information does not take the place of talking to your healthcare provider about your medical condition or your treatment.

What is ZITHROMAX?

ZITHROMAX is a macrolide antibiotic prescription medicine used in adults 18 years or older to treat certain infections caused by certain germs called bacteria. These bacterial infections include:

- acute worsening of chronic bronchitis
- acute sinus infection
- community-acquired pneumonia
- infected throat or tonsils
- skin infections
- infections of the urethra or cervix
- genital ulcers in men

ZITHROMAX is also used in children to treat:

- ear infections
- community-acquired pneumonia
- infected throat or tonsils

Azithromycin should not be taken by people who cannot tolerate oral medications because they are very ill or have certain other risk factors including:

- have cystic fibrosis
- have hospital acquired infections
- have known or suspected bacteria in the blood
- need to be in the hospital
- are elderly
- have any medical problems that can lower the ability of the immune system to fight infections

ZITHROMAX is not for viral infections such as the common cold.

It is not known if ZITHROMAX is safe and effective for genital ulcers in women.

It is not known if ZITHROMAX is safe and effective for children with ear infections, sinus infections, and community-acquired pneumonia under 6 months of age.

It is not known if ZITHROMAX is safe and effective for infected throat or tonsils in children under 2 years of age.

Who should not take ZITHROMAX?

Do not take ZITHROMAX if you:

- have had a severe allergic reaction to certain antibiotics known as macrolides or ketolides including azithromycin and erythromycin.
- have a history of cholestatic jaundice or hepatic dysfunction that happened with the use of azithromycin.

What should I tell my healthcare provider before taking ZITHROMAX?

Before you take ZITHROMAX, tell your healthcare provider if you:

- have pneumonia
- have cystic fibrosis
- have known or suspected bacteremia (bacterial infection in the blood)
- have liver or kidney problems
- have an irregular heartbeat, especially a problem called "QT prolongation"
- have a problem that causes muscle weakness (myasthenia gravis)
- have any other medical problems
- are pregnant or plan to become pregnant. It is not known if ZITHROMAX will harm your unborn baby.
- are breastfeeding or plan to breastfeed. ZITHROMAX has been reported to pass into breast milk. Talk to your healthcare provider about the best way to feed your baby while you take ZITHROMAX.

Contact your healthcare provider immediately if you are giving ZITHROMAX to a young child (less than 6 weeks of age) and he or she vomits or becomes irritable when fed.

Tell your healthcare provider about all the medicines you take, including prescription and non-prescription medicines, vitamins, and herbal supplements.

ZITHROMAX and other medicines may affect each other causing side effects. ZITHROMAX may affect the way other medicines work, and other medicines may affect how ZITHROMAX works.

Especially tell your healthcare provider if you take:

- nelfinavir
- a blood thinner (warfarin)
- digoxin
- colchicine
- phenytoin
- an antacid that contains aluminum or magnesium

Know the medicines you take. Keep a list of your medicines and show it to your healthcare provider and pharmacist when you get a new medicine.

How should I take ZITHROMAX?

- Take ZITHROMAX exactly as your healthcare provider tells you to take it.
- ZITHROMAX can be taken with or without food.
- If you take ZITHROMAX Oral Suspension, shake the bottle well just before you take it.
- Do not skip any doses of ZITHROMAX or stop taking it, even if you begin to feel better, until you finish your prescribed treatment unless you have a serious allergic reaction or your healthcare provider tells you to stop taking ZITHROMAX. "See What are the possible side effects of ZITHROMAX?" If you skip doses, or do not complete the total course of ZITHROMAX your treatment may not work as well and your infection may be harder to treat. Taking all of your ZITHROMAX doses will help lower the chance that the bacteria will become resistant to ZITHROMAX.
- If the bacteria becomes resistant to ZITHROMAX, ZITHROMAX and other antibiotic medicines may not work for you in the future.
- If you take too much ZITHROMAX, call your healthcare provider or get medical help right away.

What are the possible side effects of ZITHROMAX?

ZITHROMAX can cause serious side effects, including:

- Serious allergic reactions. Allergic reactions can happen in people taking azithromcyin the active ingredient in ZITHROMAX, even after only 1 dose. Stop taking ZITHROMAX and get emergency medical help right away if you have any of the following symptoms of a severe allergic reaction:
  - trouble breathing or swallowing
  - swelling of the lips, tongue, face
  - throat tightness, hoarseness
  - rapid heartbeat
  - faintness
  - skin rash (hives)
  - new onset of fever and swollen lymph nodes
Stop taking ZITHROMAX at the first sign of a skin rash and call your healthcare provider. Skin rash may be a sign of a more serious reaction to ZITHROMAX.
- Liver damage (hepatotoxicity). Hepatotoxicity can happen in people who take ZITHROMAX. Call your healthcare provider right away if you have unexplained symptoms such as:

- nausea or vomiting
- stomach pain
- fever
- weakness
- abdominal pain or tenderness
- itching
- unusual tiredness

- loss of appetite
- change in the color of your bowel movements
- dark colored urine
- yellowing of your skin or of the whites of your eyes

Stop taking ZITHROMAX and tell your healthcare provider right away if you have yellowing of your skin or white part of your eyes, or if you have dark urine. These can be signs of a serious reaction to ZITHROMAX (a liver problem).
2. Serious heart rhythm changes that can be life-threatening, including heart stopping (cardiac arrest), QT prolongation, torsades de pointes, feeling that your heart is pounding or racing (palpitations), chest discomfort, or irregular heartbeat.
  Tell your healthcare provider right away if you or your child feel a fast or irregular heartbeat, get dizzy or faint. ZITHROMAX may cause a rare heart problem known as prolongation of the QT interval. This condition can cause an abnormal heartbeat and can be very dangerous. The chances of this happening are higher in people:
  - who are elderly
  - with a family history of prolonged QT interval
  - with low blood potassium
  - who take certain medicines to control heart rhythm (antiarrhythmics)
3. Worsening of myasthenia gravis (a problem that causes muscle weakness). Certain antibiotics like ZITHROMAX may cause worsening of myasthenia gravis symptoms, including muscle weakness and breathing problems. Call your healthcare provider right away if you have any worsening muscle weakness or breathing problems.
4. Diarrhea. Tell your healthcare provider right away if you have watery diarrhea, diarrhea that does not go away, or bloody stools. You may experience cramping and a fever. This could happen after you have finished your ZITHROMAX.
  The most common side effects of ZITHROMAX include:
  - nausea
  - stomach pain
  - vomiting

These are not all the possible side effects of ZITHROMAX. Tell your healthcare provider about any side effect that bothers you or that does not go away.

Call your doctor for medical advice about side effects. You may report side effects to FDA at 1-800-FDA-1088.

How should I store ZITHROMAX?

- Store ZITHROMAX Tablets at 59°F to 86°F (15°C to 30°C).
- Store ZITHROMAX Oral Suspension at 41°F to 86°F (5°C to 30°C).
- Keep ZITHROMAX Oral Suspension in a tightly closed container.
- Safely throw away any medicine that is out of date or no longer needed.

Keep ZITHROMAX and all medicines out of the reach of children.

General information about the safe and effective use of ZITHROMAX.

Medicines are sometimes prescribed for purposes other than those listed in the Patient Information leaflet. Do not use ZITHROMAX for a condition for which it was not prescribed.

Do not give ZITHROMAX to other people, even if they have the same symptoms you have.

It may harm them.

This Patient Information leaflet summarizes the most important information about ZITHROMAX. If you would like more information, talk with your healthcare provider. You can ask your pharmacist or healthcare provider for information about ZITHROMAX that is written for health professionals.

For more information, go to www.zithromax.com or call 1-800-438-1986.

What are the ingredients in ZITHROMAX Tablets and Oral Suspension?

ZITHROMAX Tablets and Oral Suspension

Active ingredient: azithromycin dehydrate

ZITHROMAX Tablets:

Inactive ingredients: dibasic calcium phosphate anhydrous, pregelatinized starch, sodium croscarmellose, magnesium stearate, sodium lauryl sulfate, hypromellose, lactose, titanium dioxide, triacetin, and D&C Red #30 aluminum lake.

ZITHROMAX Oral Suspension:

Inactive ingredients: sucrose; sodium phosphate, tribasic, anhydrous; hydroxypropyl cellulose; xanthan gum; FD&C Red #40; and spray dried artificial cherry, creme de vanilla, and banana flavors.

This Patient Information has been approved by the U.S. Food and Drug Administration.

LAB-0372-7.0
Revised November 2021

PRINCIPAL DISPLAY PANEL - 250 mg - 30 Tablet Bottle Label

NDC 0069-3060-30

Pfizer

Zithromax®
(azithromycin) tablets

250 mg*

30 Tablets
Rx only

PRINCIPAL DISPLAY PANEL - 250 mg - 6 ct. Blister Pack

Zithromax®
(AZITHROMYCIN)
250 mg*
Tablets

Costs less
than most
brand name
antibiotics†

Z
Z-PAK®

A full course
of antibiotic
therapy in
5 daily doses

Rx only

6 TABLETS

PRINCIPAL DISPLAY PANEL - 250 mg - 10 ct. Blister Pack

Zithromax®
(azithromycin) Tablet

250 mg

Distributed by
PFIZER LABS
DIV OF PFIZER INC, NY, NY 10017
MADE IN USA (includes foreign content)

13074600

EXP & LOT AREA

PRINCIPAL DISPLAY PANEL - 250 mg - 18 Tablet Blister Pack

Zithromax®
(AZITHROMYCIN) 250 mg*
Tablets

Costs less than
most brand name
antibiotics†

NDC 0069-3060-75

Z-PAK®

A full course of
antibiotic therapy
in 5 daily doses

Rx only

3 CARDS x 6 TABLETS

PRINCIPAL DISPLAY PANEL - 250 mg Tablet Blister Pack Box

UNIT DOSE

NDC 0069-3060-86

Pfizer

Zithromax®
(azithromycin) tablets

250 mg*

For in-institution use only

50 Tablets
Rx only

PRINCIPAL DISPLAY PANEL - 500 mg - 30 Tablet Bottle Label

NDC 0069-3070-30

Pfizer

Zithromax®
(azithromycin) tablets

500 mg*

30 Tablets

Rx only

PRINCIPAL DISPLAY PANEL - 500 mg - 3 ct. Tablet Blister Pack

Rx only

Z

Zithromax®
(AZITHROMYCIN) 500 mg Tablets

TRI-PAK™

3 tablets x 500 mg*

A full course of
antibiotic therapy in
3 DAILY DOSES

PRINCIPAL DISPLAY PANEL - 500 mg - 3 ct. Tablet Blister Carton

NDC 0069-3070-75

Z

Zithromax®
(AZITHROMYCIN) 500 mg Tablets

TRI-PAK™

3 Cards x Three 500 mg* Tablets

PRINCIPAL DISPLAY PANEL - 300 mg Bottle Label

NDC 0069-3110-19

300 mg (15 mL when mixed)

Pfizer

Zithromax®
(azithromycin) for
oral suspension

100 mg* per 5 mL

CHERRY FLAVORED

Rx only

PRINCIPAL DISPLAY PANEL - 300 mg Bottle Carton

NDC 0069-3110-19

300 mg (15 mL when mixed)

Pfizer

Zithromax®
(azithromycin) for
oral suspension

100 mg* per 5 mL

FOR ORAL USE ONLY

CHERRY FLAVORED

Rx only

PRINCIPAL DISPLAY PANEL - 600 mg Bottle Label

NDC 0069-3120-19

600 mg (15 mL when mixed)

Pfizer

Zithromax®
(azithromycin) for
oral suspension

200 mg* per 5 mL

CHERRY FLAVORED

Rx only

PRINCIPAL DISPLAY PANEL - 600 mg Bottle Carton

NDC 0069-3120-19

600 mg (15 mL when mixed)

www.zithromax.com

Pfizer

Zithromax®
(azithromycin) for
oral suspension

200 mg* per 5 mL

FOR ORAL USE ONLY

CHERRY FLAVORED

Rx only

PRINCIPAL DISPLAY PANEL - 900 mg Bottle Label

NDC 0069-3130-19

900 mg (22.5 mL when mixed)

Pfizer

Zithromax®
(azithromycin) for
oral suspension

200 mg* per 5 mL

CHERRY FLAVORED

Rx only

PRINCIPAL DISPLAY PANEL - 900 mg Bottle Carton

NDC 0069-3130-19

900 mg (22.5 mL when mixed)

Pfizer

Zithromax®
(azithromycin) for
oral suspension

200 mg* per 5 mL

FOR ORAL USE ONLY

CHERRY FLAVORED

Rx only

PRINCIPAL DISPLAY PANEL - 1200 mg Bottle Label

NDC 0069-3140-19

1200 mg (30 mL when mixed)

Pfizer

Zithromax®
(azithromycin) for
oral suspension

200 mg* per 5 mL

CHERRY FLAVORED

Rx only

PRINCIPAL DISPLAY PANEL - 1200 mg Bottle Carton

NDC 0069-3140-19

1200 mg (30 mL when mixed)

Pfizer

Zithromax®
(azithromycin) for
oral suspension

200 mg* per 5 mL

FOR ORAL USE ONLY

CHERRY FLAVORED

Rx only